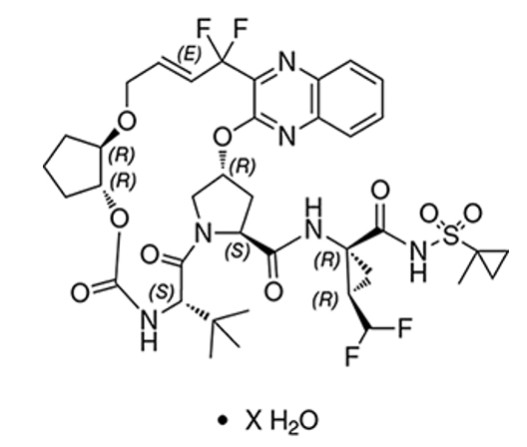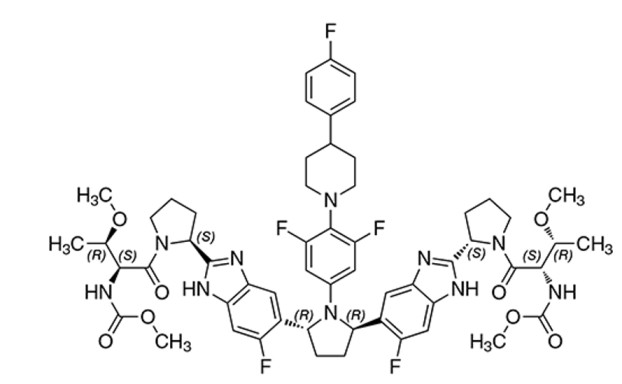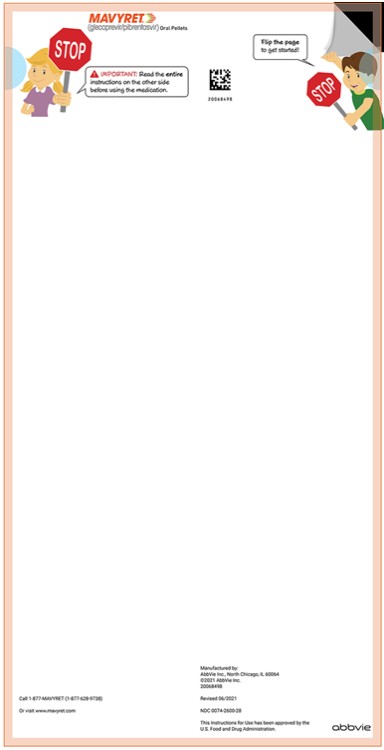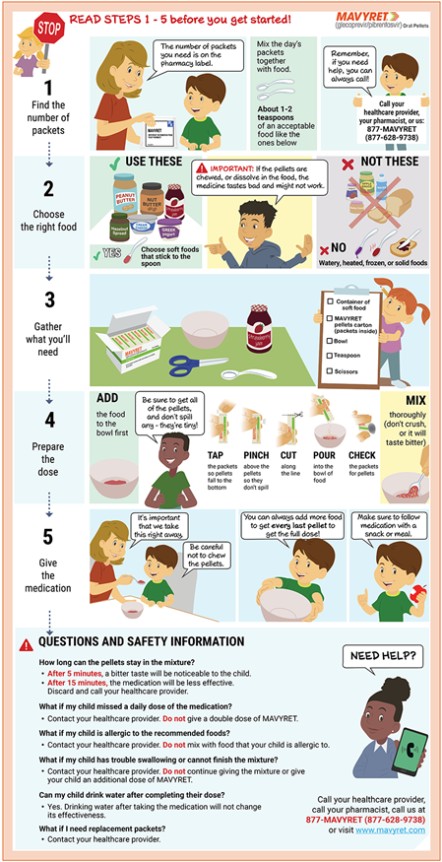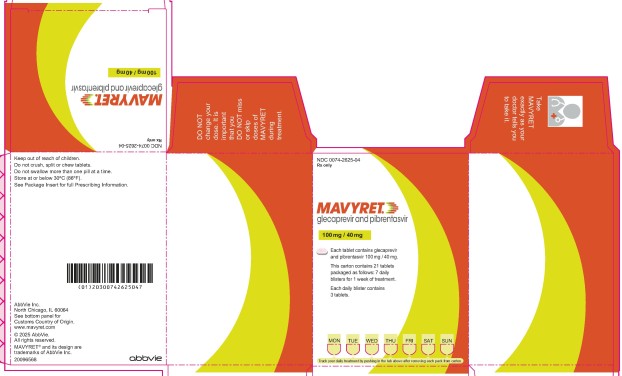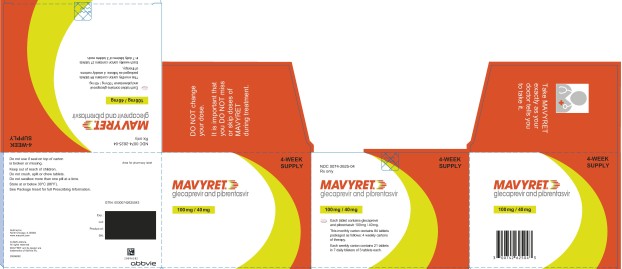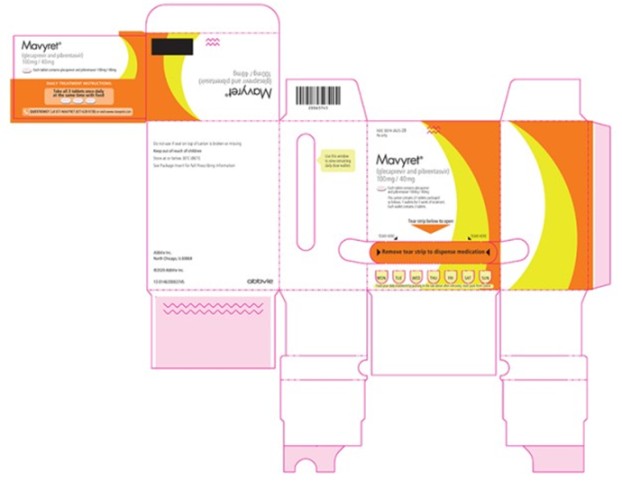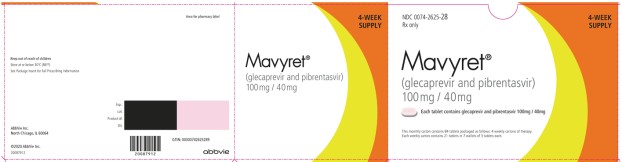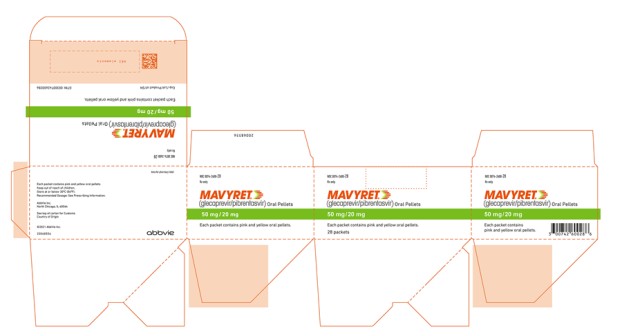 DRUG LABEL: Mavyret
NDC: 0074-2625 | Form: TABLET, FILM COATED
Manufacturer: AbbVie Inc.
Category: prescription | Type: HUMAN PRESCRIPTION DRUG LABEL
Date: 20250610

ACTIVE INGREDIENTS: PIBRENTASVIR 40 mg/1 1; GLECAPREVIR 100 mg/1 1
INACTIVE INGREDIENTS: VITAMIN E POLYETHYLENE GLYCOL SUCCINATE; SILICON DIOXIDE; CROSCARMELLOSE SODIUM; SODIUM STEARYL FUMARATE; HYPROMELLOSE 2910 (15 MPA.S); LACTOSE MONOHYDRATE; POLYETHYLENE GLYCOL 3350; FERRIC OXIDE RED; TITANIUM DIOXIDE; COPOVIDONE K25-31; PROPYLENE GLYCOL MONOCAPRYLATE

HIGHLIGHTS OF PRESCRIBING INFORMATION

These highlights do not include all the information needed to use MAVYRET safely and effectively. See full prescribing information for MAVYRET.
MAVYRET® (glecaprevir and pibrentasvir) tablets, for oral use
MAVYRET® (glecaprevir and pibrentasvir) oral pellets
Initial U.S. Approval: 2017

RECENT MAJOR CHANGES

Indications and Usage (1) | 6/2025
Dosage and Administration (2.2) | 6/2025

WARNING: RISK OF HEPATITIS B VIRUS REACTIVATION IN PATIENTS COINFECTED WITH HCV AND HBV

See full prescribing information for complete boxed warning.

Hepatitis B virus (HBV) reactivation has been reported, in some cases resulting in fulminant hepatitis, hepatic failure, and death. (5.1)

1 INDICATIONS AND USAGE

- MAVYRET is a fixed-dose combination of glecaprevir, a hepatitis C virus (HCV) NS3/4A protease inhibitor, and pibrentasvir, an HCV NS5A inhibitor, and is indicated for the treatment of adult and pediatric patients 3 years and older with acute or chronic HCV genotype (GT) 1, 2, 3, 4, 5 or 6 infection without cirrhosis or with compensated cirrhosis (Child-Pugh A).
- MAVYRET is indicated for the treatment of adult and pediatric patients 3 years and older with HCV genotype 1 infection, who previously have been treated with a regimen containing an HCV NS5A inhibitor or an NS3/4A protease inhibitor, but not both. (1)

2 DOSAGE AND ADMINISTRATION

- Testing Prior to the Initiation of Therapy: Test all patients for HBV infection by measuring HBsAg and anti-HBc. (2.1)
- See recommended treatment duration for patients 3 years and older in tables below. (2.2)

Treatment-Naïve Patients^1

HCV Genotype | Treatment Duration
 | No Cirrhosis | Compensated Cirrhosis (Child-Pugh A)
1, 2, 3, 4, 5, or 6 | 8 weeks | 8 weeks

1. Treatment-naïve patients are those who have not received treatment for the current infection.

Treatment-Experienced Patients^1

 |  | Treatment Duration
HCV Genotype | Patients Previously Treated With a Regimen Containing: | No Cirrhosis | Compensated Cirrhosis (Child-Pugh A)
1 | An NS5A inhibitor^2 without prior treatment with an NS3/4A protease inhibitor (PI) | 16 weeks | 16 weeks
 | An NS3/4A PI^3 without prior treatment with an NS5A inhibitor | 12 weeks | 12 weeks
1, 2, 4, 5, or 6 | PRS^4 | 8 weeks | 12 weeks
3 | PRS^4 | 16 weeks | 16 weeks
1. Treatment-experienced patients are those who previously received treatment for the current infection.
2. Treated with prior regimens containing ledipasvir and sofosbuvir or daclatasvir with (peg) interferon and ribavirin.
3. Treated with prior regimens containing simeprevir and sofosbuvir, or simeprevir, boceprevir, or telaprevir with (peg) interferon and ribavirin.
4. PRS=Prior treatment experience with regimens containing (peg) interferon, ribavirin, and/or sofosbuvir, but no prior treatment experience with an HCV NS3/4A PI or NS5A inhibitor.

- Recommended dosage in adults: Three tablets taken at the same time orally once daily (total daily dose: glecaprevir 300 mg and pibrentasvir 120 mg) with food. (2.3)
- Recommended dosage in pediatric patients 3 years and older:
  - Pediatric Patients 3 Years to Less than 12 Years Old: Dosing is based on weight. Refer to Table 3 of the full prescribing information for specific dosing guidelines based on body weight. (2.4) Instructions for Use should be followed for preparation and administration of MAVYRET oral pellets. (2.5)
  - Pediatric Patients 12 Years of Age and Older, or Pediatric Patients Weighing at Least 45 kg: three tablets taken at the same time orally once daily (total daily dose: glecaprevir 300 mg and pibrentasvir 120 mg) with food. (2.4)
- HCV/HIV-1 co-infection and patients with any degree of renal impairment: Follow the dosage recommendations in the tables above. (2.2)
- Liver or Kidney Transplant Recipients: MAVYRET is recommended for 12 weeks in patients 3 years and older who are liver or kidney transplant recipients. A 16-week treatment duration is recommended in genotype 1-infected patients who are NS5A inhibitor-experienced without prior treatment with an NS3/4A PI or in genotype 3-infected patients who are PRS treatment-experienced. (2.6)

3 DOSAGE FORMS AND STRENGTHS

- Tablets: 100 mg glecaprevir and 40 mg pibrentasvir. (3)
- Oral Pellets: 50 mg glecaprevir and 20 mg pibrentasvir. (3)

4 CONTRAINDICATIONS

- Patients with moderate or severe hepatic impairment (Child-Pugh B or C) or those with any history of prior hepatic decompensation. (4, 5.2)
- Coadministration with atazanavir or rifampin. (4)

5 WARNINGS AND PRECAUTIONS

- Risk of Hepatitis B Virus Reactivation: Test all patients for evidence of current or prior HBV infection before initiation of HCV treatment. Monitor HCV/HBV coinfected patients for HBV reactivation and hepatitis flare during HCV treatment and post-treatment follow-up. Initiate appropriate patient management for HBV infection as clinically indicated. (5.1)
- Risk of Hepatic Decompensation/Failure in Patients with Evidence of Advanced Liver Disease: Hepatic decompensation/failure, including fatal outcomes, have been reported mostly in patients with cirrhosis and baseline moderate or severe liver impairment (Child-Pugh B or C). Monitor for clinical and laboratory evidence of hepatic decompensation. Discontinue MAVYRET in patients who develop evidence of hepatic decompensation/failure. (5.2)

6 ADVERSE REACTIONS

In subjects receiving MAVYRET, the most commonly reported adverse reactions (greater than 10%) are headache and fatigue. (6.1)

To report SUSPECTED ADVERSE REACTIONS, contact AbbVie Inc. at 1-800-633-9110 or FDA at 1-800-FDA-1088 or www.fda.gov/medwatch.

7 DRUG INTERACTIONS

- Carbamazepine, efavirenz, and St. John’s wort may decrease concentrations of glecaprevir and pibrentasvir. Coadministration of carbamazepine, efavirenz containing regimens, and St. John’s wort with MAVYRET is not recommended. (5.3)
- Clearance of HCV infection with direct-acting antivirals may lead to changes in hepatic function, which may impact safe and effective use of concomitant medications. Frequent monitoring of relevant laboratory parameters (INR or blood glucose) and dose adjustments of certain concomitant medications may be necessary. (7.3)
- Medication- Assisted Treatment (MAT) for Opioid Use Disorder. (7.4)
- Consult the full prescribing information prior to and during treatment for potential drug interactions. (4, 7, 12.3)

FULL PRESCRIBING INFORMATION

WARNING: RISK OF HEPATITIS B VIRUS REACTIVATION IN PATIENTS COINFECTED WITH HCV AND HBV

Test all patients for evidence of current or prior hepatitis B virus (HBV) infection before initiating treatment with MAVYRET. HBV reactivation has been reported in HCV/HBV coinfected patients who were undergoing or had completed treatment with HCV direct-acting antivirals and were not receiving HBV antiviral therapy. Some cases have resulted in fulminant hepatitis, hepatic failure, and death. Monitor HCV/HBV coinfected patients for hepatitis flare or HBV reactivation during HCV treatment and post-treatment follow-up. Initiate appropriate patient management for HBV infection as clinically indicated [see Warnings and Precautions (5.1)].

1 INDICATIONS AND USAGE

MAVYRET is indicated for the treatment of adult and pediatric patients 3 years and older with acute or chronic hepatitis C virus (HCV) genotype 1, 2, 3, 4, 5 or 6 infection without cirrhosis or with compensated cirrhosis (Child-Pugh A).

MAVYRET is indicated for the treatment of adult and pediatric patients 3 years and older with HCV genotype 1 infection, who previously have been treated with a regimen containing an HCV NS5A inhibitor or an NS3/4A protease inhibitor (PI), but not both [see Dosage and Administration (2.2) and Clinical Studies (14)].

2 DOSAGE AND ADMINISTRATION

2.1 Testing Prior to the Initiation of Therapy

Test all patients for evidence of current or prior HBV infection by measuring hepatitis B surface antigen (HBsAg) and hepatitis B core antibody (anti-HBc) before initiating HCV treatment with MAVYRET [see Warnings and Precautions (5.1)].

2.2 Recommended Treatment Duration in Patients 3 Years and Older

Tables 1 and 2 provide the recommended MAVYRET treatment duration based on the patient population in HCV mono-infected and HCV/HIV-1 co-infected patients with compensated liver disease (with or without cirrhosis) and with or without renal impairment including patients receiving dialysis [see Contraindications (4) and Clinical Studies (14)]. Refer to Drug Interactions (7) for dosage recommendations for concomitant HIV-1 antiviral drugs.

Table 1. Recommended Duration for Treatment-Naïve Patients^1
HCV Genotype | Treatment Duration
 | No Cirrhosis | Compensated Cirrhosis (Child-Pugh A)
1, 2, 3, 4, 5, or 6 | 8 weeks | 8 weeks

1. Treatment-naïve patients are those who have not received treatment for the current infection.

Table 2. Recommended Duration for Treatment-Experienced Patients^1
 |  | Treatment Duration
HCV Genotype | Patients Previously Treated with a Regimen Containing: | No Cirrhosis | Compensated Cirrhosis (Child-Pugh A)
1 | An NS5A inhibitor^2 without prior treatment with an NS3/4A protease inhibitor (PI) | 16 weeks | 16 weeks
 | An NS3/4A PI^3 without prior treatment with an NS5A inhibitor | 12 weeks | 12 weeks
1, 2, 4, 5, or 6 | PRS^4 | 8 weeks | 12 weeks
3 | PRS^4 | 16 weeks | 16 weeks
1. Treatment-experienced patients are those who previously received treatment for the current infection.
2. In clinical trials, subjects were treated with prior regimens containing ledipasvir and sofosbuvir or daclatasvir with (peg)interferon and ribavirin.
3. In clinical trials, subjects were treated with prior regimens containing simeprevir and sofosbuvir, or simeprevir, boceprevir, or telaprevir with (peg)interferon and ribavirin.
4. PRS=Prior treatment experience with regimens containing (peg)interferon, ribavirin, and/or sofosbuvir, but no prior treatment experience with an HCV NS3/4A PI or NS5A inhibitor.

2.3 Recommended Dosage in Adults

MAVYRET tablets are a fixed combination drug product containing glecaprevir 100 mg and pibrentasvir 40 mg in each tablet.

The recommended oral dosage of MAVYRET in adults is 3 tablets taken at the same time once daily with food (total daily dose: glecaprevir 300 mg and pibrentasvir 120 mg) [see Clinical Pharmacology (12.3)].

2.4 Recommended Dosage in Pediatric Patients 3 Years of Age and Older

The recommended dosage of MAVYRET in pediatric patients 3 to less than 12 years of age is based on weight. MAVYRET oral pellets are recommended for pediatric patients 3 to less than 12 years old weighing less than 45 kg. MAVYRET oral pellets in packets are a fixed combination drug product containing glecaprevir 50 mg and pibrentasvir 20 mg in each packet.

The recommended dosage of MAVYRET in pediatric patients 12 years of age and older, or in pediatric patients weighing at least 45 kg, is three tablets taken at the same time once daily with food (total daily dose: glecaprevir 300 mg and pibrentasvir 120 mg).

The dosages for pediatric patients are shown in Table 3.

Table 3. Recommended Dosage in Pediatric Patients 3 Years of Age and Older
Body Weight (kg) or Age (yrs) | Daily Dose of glecaprevir/pibrentasvir | Dosing of MAVYRET
Less than 20 kg | 150 mg/60 mg per day | Three 50 mg/20 mg packets of oral pellets once daily
20 kg to less than 30 kg | 200 mg/80 mg per day | Four 50 mg/20 mg packets of oral pellets once daily
30 kg to less than 45 kg | 250 mg/100 mg per day | Five 50 mg/20 mg packets of oral pellets once daily
45 kg and greater OR 12 years of age and older | 300 mg/120 mg per day | Three 100 mg/40 mg tablets once daily^1 (see Recommended Dosage in Adults)
^1 Pediatric patients weighing 45 kg and greater who are unable to swallow tablets may take six 50 mg/20 mg packets of oral pellets once daily. Dosing with oral pellets has not been studied for pediatric patients weighing greater than 45 kg [see Clinical Pharmacology (12.3)].

2.5 Preparation and Administration of Oral Pellets

See the MAVYRET oral pellets full Instructions for Use for details on the preparation and administration.

- The oral pellets should be taken together, with food, once daily. In addition, the oral pellets for the total daily dose should be sprinkled on a small amount of soft food with a low water content that will stick to a spoon and should be swallowed without chewing (e.g., peanut butter, chocolate hazelnut spread, cream cheese, thick jam, or Greek yogurt).
- The entire mixture of food and oral pellets should be swallowed within 15 minutes of preparation; the oral pellets should not be crushed or chewed.
- Liquids or foods that would drip or slide off the spoon are not recommended as the drug may dissolve quickly and become less effective.

2.6 Liver or Kidney Transplant Recipients

MAVYRET is recommended for 12 weeks in patients 3 years and older who are liver or kidney transplant recipients. A 16-week treatment duration is recommended in genotype 1-infected patients who are NS5A inhibitor-experienced without prior treatment with an NS3/4A protease inhibitor or in genotype 3-infected patients who are PRS treatment-experienced [see Clinical Studies (14.8)].

2.7 Hepatic Impairment

MAVYRET is contraindicated in patients with moderate or severe hepatic impairment (Child-Pugh B or C) or those with any history of prior hepatic decompensation [see Contraindications (4), Warnings and Precautions (5.2), Use in Specific Populations (8.7) and Clinical Pharmacology (12.3)].

3 DOSAGE FORMS AND STRENGTHS

MAVYRET is available as tablets or pellets for oral use.

- Tablets: pink, oblong-shaped, film-coated, and debossed with “NXT” on one side. Each tablet contains 100 mg glecaprevir and 40 mg of pibrentasvir.
- Oral pellets: pink and yellow coated pellets in unit-dose packets. Each packet contains 50 mg glecaprevir and 20 mg pibrentasvir.

4 CONTRAINDICATIONS

- MAVYRET is contraindicated in patients with moderate or severe hepatic impairment (Child-Pugh B or C) or those with any history of prior hepatic decompensation [see Warnings and Precautions (5.2), Use in Specific Populations (8.7) and Clinical Pharmacology (12.3)].
- MAVYRET is contraindicated with atazanavir or rifampin [see Drug Interaction (7.3) and Clinical Pharmacology (12.3)].

5 WARNINGS AND PRECAUTIONS

5.1 Risk of Hepatitis B Virus Reactivation in Patients Coinfected with HCV and HBV

Hepatitis B virus (HBV) reactivation has been reported in HCV/HBV coinfected patients who were undergoing or had completed treatment with HCV direct-acting antivirals, and who were not receiving HBV antiviral therapy. Some cases have resulted in fulminant hepatitis, hepatic failure and death. Cases have been reported in patients who are HBsAg positive and also in patients with serologic evidence of resolved HBV infection (i.e., HBsAg negative and anti-HBc positive). HBV reactivation has also been reported in patients receiving certain immunosuppressant or chemotherapeutic agents; the risk of HBV reactivation associated with treatment with HCV direct-acting antivirals may be increased in these patients.

HBV reactivation is characterized as an abrupt increase in HBV replication manifesting as a rapid increase in serum HBV DNA level. In patients with resolved HBV infection reappearance of HBsAg can occur. Reactivation of HBV replication may be accompanied by hepatitis, i.e., increase in aminotransferase levels and, in severe cases, increases in bilirubin levels, liver failure, and death can occur.

Test all patients for evidence of current or prior HBV infection by measuring HBsAg and anti- HBc before initiating HCV treatment with MAVYRET. In patients with serologic evidence of HBV infection, monitor for clinical and laboratory signs of hepatitis flare or HBV reactivation during HCV treatment with MAVYRET and during post-treatment follow-up. Initiate appropriate patient management for HBV infection as clinically indicated.

5.2 Risk of Hepatic Decompensation/Failure in Patients with Evidence of Advanced Liver Disease

Postmarketing cases of hepatic decompensation/failure, including those with fatal outcomes, have been reported in patients treated with HCV NS3/4A protease inhibitor-containing regimens, including MAVYRET. Because these events are reported voluntarily from a population of uncertain size, it is not always possible to reliably estimate their frequency or establish a causal relationship to drug exposure.

The majority of patients with severe outcomes had evidence of advanced liver disease with moderate or severe hepatic impairment (Child-Pugh B or C) prior to initiating therapy with MAVYRET, including some patients reported as having compensated cirrhosis with mild liver impairment (Child-Pugh A) at baseline but with a prior decompensation event (i.e., prior history of ascites, variceal bleeding, encephalopathy). Rare cases of hepatic decompensation/failure were reported in patients without cirrhosis or with compensated cirrhosis (Child-Pugh A); many of these patients had evidence of portal hypertension. Events also occurred in patients taking a concomitant medication not recommended for coadministration, or in patients with confounding factors such as serious liver-related medical or surgical comorbidities. Cases typically occurred within the first 4 weeks of treatment (median of 27 days).

In patients with compensated cirrhosis (Child-Pugh A) or evidence of advanced liver disease such as portal hypertension, perform hepatic laboratory testing as clinically indicated; and monitor for signs and symptoms of hepatic decompensation such as the presence of jaundice, ascites, hepatic encephalopathy, and variceal hemorrhage. Discontinue MAVYRET in patients who develop evidence of hepatic decompensation/failure.

MAVYRET is contraindicated in patients with moderate to severe hepatic impairment (Child-Pugh B or C) or those with any history of prior hepatic decompensation [see Contraindications (4), Adverse Reactions (6.1), Use in Specific Populations (8.7), and Clinical Pharmacology (12.3)].

5.3 Risk of Reduced Therapeutic Effect Due to Concomitant Use of MAVYRET with Carbamazepine, Efavirenz Containing Regimens, or St. John’s Wort

Carbamazepine, efavirenz, and St. John’s wort may significantly decrease plasma concentrations of glecaprevir and pibrentasvir, leading to reduced therapeutic effect of MAVYRET. The use of these agents with MAVYRET is not recommended.

6 ADVERSE REACTIONS

6.1 Clinical Trials Experience

Because clinical trials are conducted under widely varying conditions, adverse reaction rates observed in clinical trials of MAVYRET cannot be directly compared to rates in the clinical trials of another drug and may not reflect the rates observed in practice.

Overall Adverse Reactions in Subjects with Chronic HCV Infection without Cirrhosis or with Compensated Cirrhosis (Child-Pugh A)

The adverse reactions data for MAVYRET in subjects without cirrhosis or with compensated cirrhosis (Child-Pugh A) were derived from nine registrational Phase 2 and 3 trials which evaluated approximately 2,300 adults infected with genotype 1, 2, 3, 4, 5, or 6 HCV who received MAVYRET for 8, 12 or 16 weeks [see Clinical Studies (14)].

The overall proportion of subjects who permanently discontinued treatment due to adverse reactions was 0.1% for subjects who received MAVYRET for 8, 12 or 16 weeks.

The most common adverse reactions, all grades, observed in greater than or equal to 5% of subjects receiving 8, 12, or 16 weeks of treatment with MAVYRET were headache (13%), fatigue (11%), and nausea (8%). In subjects receiving MAVYRET who experienced adverse reactions, 80% had an adverse reaction of mild severity (Grade 1). One subject experienced a serious adverse reaction.

Adverse reactions (type and severity) were similar for subjects receiving MAVYRET for 8, 12 or 16 weeks. The type and severity of adverse reactions in subjects with compensated cirrhosis (Child-Pugh A) were similar to those seen in subjects without cirrhosis.

Adverse Reactions in Subjects with Chronic HCV Infection without Cirrhosis

ENDURANCE-2

Among 302 treatment-naïve or PRS treatment-experienced, HCV genotype 2-infected adults without cirrhosis enrolled in ENDURANCE-2, adverse reactions (all intensity) occurring in at least 5% of subjects treated with MAVYRET for 12 weeks are presented in Table 4. In subjects treated with MAVYRET for 12 weeks, 32% reported an adverse reaction, of which 98% had adverse reactions of mild or moderate severity. No subjects treated with MAVYRET or placebo in ENDURANCE-2 permanently discontinued treatment due to an adverse drug reaction.

Table 4. Adverse Reactions Reported in ≥5% of Treatment-Naïve and PRS-Experienced Adults without Cirrhosis Receiving MAVYRET for 12 Weeks in ENDURANCE-2
Adverse Reaction | MAVYRET 12 Weeks (N = 202) % | Placebo 12 Weeks (N = 100) %
Headache | 9 | 6
Nausea | 6 | 2
Diarrhea | 5 | 2

ENDURANCE-3

Among 505 treatment-naïve, HCV genotype 3-infected adults without cirrhosis enrolled in ENDURANCE-3, adverse reactions (all intensity) occurring in at least 5% of subjects treated with MAVYRET for 8 or 12 weeks are presented in Table 5. In subjects treated with MAVYRET, 45% reported an adverse reaction, of which 99% had adverse reactions of mild or moderate severity. The proportion of subjects who permanently discontinued treatment due to adverse reactions was 0%, < 1% and 1% for the MAVYRET 8-week arm, MAVYRET 12 week arm and DCV + SOF arm, respectively.

Table 5. Adverse Reactions Reported in ≥5% of Treatment-Naïve Adults without Cirrhosis Receiving MAVYRET for 8 Weeks or 12 Weeks in ENDURANCE-3
Adverse Reaction | MAVYRET* 8 Weeks (N = 157) % | MAVYRET 12 Weeks (N = 233) % | DCV^1 + SOF^2 12 Weeks (N = 115) %
Headache | 16 | 17 | 15
Fatigue | 11 | 14 | 12
Nausea | 9 | 12 | 12
Diarrhea | 7 | 3 | 3
^1 DCV=daclatasvir
^2 SOF=sofosbuvir
* The 8-week arm was a non-randomized treatment arm.

Adverse Reactions in Subjects with Chronic HCV Infection with Compensated Cirrhosis (Child-Pugh A)

The safety of MAVYRET in HCV GT 1, 2, 3, 4, 5, or 6 subjects with compensated cirrhosis is based on data from 288 adults from the Phase 2/3 registrational trials treated with MAVYRET for 12 or more weeks and 343 adults from EXPEDITION-8 treated with MAVYRET for 8 weeks. The adverse reactions observed were generally consistent with those observed in clinical studies of MAVYRET in non-cirrhotic subjects [see Clinical Studies (14)].

In the Phase 2/3 registrational trials, the adverse reactions reported in greater than or equal to 5% of compensated cirrhotic subjects (n=288) treated across all durations of MAVYRET were fatigue (15%), headache (14%), nausea (8%), diarrhea (6%), and pruritus (6%). In EXPEDITION-8, the adverse reactions reported in greater than or equal to 5% of compensated cirrhotic subjects (n=343) were fatigue (8%), pruritus (7%), and headache (6%). No subjects with compensated cirrhosis in the Phase 2/3 registrational trials (without severe renal impairment) or in EXPEDITION-8 discontinued treatment with MAVYRET due to an adverse reaction.

Adverse Reactions in Subjects with Chronic HCV Infection with Severe Renal Impairment Including Those on Dialysis

The safety of MAVYRET in subjects with chronic kidney disease (Stage 4 or Stage 5 including subjects on dialysis) with genotypes 1, 2, 3, 4, 5 or 6 chronic HCV infection without cirrhosis or with compensated cirrhosis (Child-Pugh A) was assessed in 104 adults (EXPEDITION-4) who received MAVYRET for 12 weeks. The most common adverse reactions observed in greater than or equal to 5% of subjects receiving 12 weeks of treatment with MAVYRET were pruritus (17%), fatigue (12%), nausea (9%), asthenia (7%), and headache (6%). In subjects treated with MAVYRET who reported an adverse reaction, 90% had adverse reactions of mild or moderate severity (Grade 1 or 2). The proportion of subjects who permanently discontinued treatment due to adverse reactions was 2%.

Adverse Reactions in Subjects with Chronic HCV Infection Co-Infected with HIV-1

The safety of MAVYRET in subjects with HIV-1 co-infection with genotypes 1, 2, 3, 4 or 6 chronic HCV infection without cirrhosis or with compensated cirrhosis (Child-Pugh A) was assessed in 153 adults (EXPEDITION-2) who received MAVYRET for 8 or 12 weeks. Thirty-three subjects with HIV-1 coinfection also received 8 or 12 weeks of therapy in ENDURANCE-1.

The overall safety profile in HCV/HIV-1 co-infected subjects (ENDURANCE-1 and EXPEDITION-2) was similar to that observed in HCV mono-infected subjects. Adverse reactions observed in greater than or equal to 5% of subjects receiving MAVYRET in EXPEDITION-2 for 8 or 12 weeks were fatigue (10%), nausea (8%), and headache (5%).

Adverse Reactions in Subjects with Chronic HCV Infection with Liver or Kidney Transplant

The safety of MAVYRET was assessed in 100 adult post-liver or -kidney transplant recipients with genotypes 1, 2, 3, 4, or 6 chronic HCV infection without cirrhosis (MAGELLAN-2). The overall safety profile in transplant recipients was similar to that observed in subjects in the Phase 2 and 3 studies, without a history of transplantation. Adverse reactions observed in greater than or equal to 5% of subjects receiving MAVYRET for 12 weeks were headache (17%), fatigue (16%), nausea (8%) and pruritus (7%). In subjects treated with MAVYRET who reported an adverse reaction, 81% had adverse reactions of mild severity. Two percent of subjects experienced a serious adverse reaction, and no subjects permanently discontinued treatment due to adverse reactions.

Adverse Reactions in People Who Inject Drugs (PWID) and those on Medication-Assisted Treatment (MAT) for Opioid Use Disorder with Chronic HCV Infection

PWID

The safety of MAVYRET in PWID with chronic HCV GT 1, 2, 3, 4, 5, or 6 infection is based on data from adults and adolescents in Phase 2 and 3 trials in which 62 subjects identified as current/recent PWID (defined as self-reported injection drug use within the last 12 months prior to starting MAVYRET) and 3,282 subjects reported no injection drug use (non-PWID).

Among current/recent PWID, adverse reactions observed in greater than or equal to 5% of subjects were fatigue (16%), headache (13%), diarrhea (6%), and nausea (6%). Among non-PWID subjects, adverse reactions observed in greater than or equal to 5% were headache (7%) and fatigue (6%). Serious adverse reactions and/or adverse reactions leading to treatment discontinuation occurred in one current/recent PWID subject (2%) compared to less than 1% in non-PWID subjects [see Use in Specific Populations (8.8) and Clinical Studies (14.9)].

MAT

The safety of MAVYRET in subjects with chronic HCV GT 1, 2, 3, 4, 5, or 6 infection reporting concomitant use of MAT for opioid use disorder is based on data from adults and adolescents in Phase 2 and 3 trials in which 225 subjects reported concomitant use of MAT and 4,098 subjects reported no concomitant use of MAT.

Among subjects on MAT, adverse reactions observed in greater than or equal to 5% were headache (15%), fatigue (12%), nausea (11%), and diarrhea (6%). Among subjects who were not on MAT, adverse reactions observed in greater than or equal to 5% were headache (9%), fatigue (8%), and nausea (5%). Serious adverse reactions and/or adverse reactions leading to treatment discontinuation were not observed among subjects on MAT and were experienced by less than 1% of subjects not on MAT [see Use in Specific Populations (8.8) and Clinical Studies (14.9)].

Adverse Reactions in Subjects with Acute HCV Infection

The safety of MAVYRET in subjects with acute HCV GT 1, 2, 3, or 4 infection was assessed in 286 adults who received MAVYRET for 8 weeks. Among these subjects, 142 had HIV-1 co-infection, 41 identified as current/recent PWID, and 21 reported concomitant use of MAT. At baseline, 49% of subjects had ALT elevations greater than 3 x upper limit of normal (ULN), 13% had ALT elevations greater than 10 x ULN, and 12% had total bilirubin elevations greater than ULN. The overall safety profile in these subjects was similar to that observed in subjects with chronic HCV infection. Serious adverse reactions and/or adverse reactions leading to treatment discontinuation were not observed among subjects with acute HCV infection.

The most commonly reported adverse reactions were fatigue (3%), asthenia (2%), headache (2%) and diarrhea (2%) [see Use in Specific Populations (8.4), Use in Specific Populations (8.5) Clinical Studies (14.11)].

Adverse Reactions in Pediatric Subjects 3 Years and Older with Chronic HCV Infection

The safety of MAVYRET in HCV GT 1, 2, 3, or 4 infected adolescents is based on data from a Phase 2/3 open-label trial in 47 subjects aged 12 years to less than 18 years without cirrhosis treated with MAVYRET for 8 or 16 weeks (DORA-Part 1). The adverse reactions observed in subjects 12 years to less than 18 years of age were consistent with those observed in clinical trials of MAVYRET in adults. The only adverse reaction observed in greater than or equal to 5% of subjects receiving MAVYRET in DORA Part 1 was fatigue (6%). No subjects discontinued or interrupted treatment with MAVYRET due to an adverse reaction.

The safety of MAVYRET in HCV GT 1, 2, 3, or 4 infected pediatric subjects aged 3 years to less than 12 years is based on data from a Phase 2/3 open-label trial in 80 subjects aged 3 to less than 12 years without cirrhosis treated with weight-based MAVYRET oral pellets in packets for 8, 12 or 16 weeks (DORA-Part 2). The adverse reactions observed in subjects 3 years to less than 12 years of age were consistent with those observed in clinical trials of MAVYRET in adults with the exception of vomiting (occurring at 8%), rash, and abdominal pain upper (each occurring at 4%) which were observed more frequently in pediatric subjects less than 12 years of age compared to adults. Other adverse reactions observed in greater than or equal to 5% of subjects receiving MAVYRET in DORA-Part 2 include fatigue and headache, each occurring at 8%. One subject discontinued treatment due to an adverse reaction of erythematous rash (Grade 3). All other adverse reactions were Grade 1 or 2 and no subjects interrupted treatment due to an adverse reaction [see Use in Specific Populations (8.4), Clinical Studies (14.10)].

Laboratory Abnormalities

Serum bilirubin elevations in subjects with chronic HCV infection

Elevations of total bilirubin at least 2 times the ULN occurred in 3.5% of adult subjects treated with MAVYRET versus 0% in placebo; these elevations were observed in 1.2% of adult subjects across the Phase 2 and 3 trials.

In adult subjects with compensated cirrhosis (Child-Pugh A), 17% experienced early, transient post-baseline elevations of bilirubin above the ULN. These bilirubin elevations were typically less than 2 × ULN, generally occurred within the first 2 weeks of treatment and resolved with continued treatment. The subjects with compensated cirrhosis and bilirubin elevations did not have concurrent increases in ALT or AST, or signs of liver decompensation or failure, and these laboratory events did not lead to treatment discontinuation. MAVYRET inhibits OATP1B1/3 and is a weak inhibitor of UGT1A1 and may have the potential to impact bilirubin transport and metabolism, including direct and indirect bilirubin. Few subjects experienced jaundice or ocular icterus and total bilirubin levels decreased after completing MAVYRET.

Liver tests in subjects with acute HCV infection

Elevations of total bilirubin at least 2 times ULN occurred in 2.8% of subjects treated with MAVYRET. Subjects with total bilirubin elevations did not have concurrent increases in ALT or AST, or signs of liver decompensation or failure, and these laboratory events did not lead to treatment discontinuation. All subjects with baseline ALT > 3 × ULN improved from baseline by the final treatment visit.

6.2 Postmarketing Experience

The following adverse reactions have been identified during post-approval use of MAVYRET. Because these reactions are reported voluntarily from a population of uncertain size, it is not always possible to reliably estimate their frequency or establish a causal relationship to drug exposure.

Skin and Subcutaneous Tissue Disorders: Angioedema

Hepatobiliary Disorders: Hepatic decompensation, hepatic failure [see Warnings and Precautions (5.2)].

7 DRUG INTERACTIONS

7.1 Mechanisms for the Potential Effect of MAVYRET on Other Drugs

Glecaprevir and pibrentasvir are inhibitors of P-glycoprotein (P-gp), breast cancer resistance protein (BCRP), and organic anion transporting polypeptide (OATP) 1B1/3. Coadministration with MAVYRET may increase plasma concentration of drugs that are substrates of P-gp, BCRP, OATP1B1 or OATP1B3. Glecaprevir and pibrentasvir are weak inhibitors of cytochrome P450 (CYP) 3A, CYP1A2, and uridine glucuronosyltransferase (UGT) 1A1.

7.2 Mechanisms for the Potential Effect of Other Drugs on MAVYRET

Glecaprevir and pibrentasvir are substrates of P-gp and/or BCRP. Glecaprevir is a substrate of OATP1B1/3. Coadministration of MAVYRET with drugs that inhibit hepatic P-gp, BCRP, or OATP1B1/3 may increase the plasma concentrations of glecaprevir and/or pibrentasvir.

Coadministration of MAVYRET with drugs that induce P-gp/CYP3A may decrease glecaprevir and pibrentasvir plasma concentrations.

Carbamazepine, phenytoin, efavirenz, and St. John’s wort may significantly decrease plasma concentrations of glecaprevir and pibrentasvir, leading to reduced therapeutic effect of MAVYRET. The use of these agents with MAVYRET is not recommended [see Warnings and Precautions (5.3) and Clinical Pharmacology (12.3)].

7.3 Established and Other Potential Drug Interactions

Clearance of HCV infection with direct-acting antivirals may lead to changes in hepatic function, which may impact the safe and effective use of concomitant medications. For example, altered blood glucose control resulting in serious symptomatic hypoglycemia has been reported in diabetic patients in postmarketing case reports and published epidemiological studies. Management of hypoglycemia in these cases required either discontinuation or dose modification of concomitant medications used for diabetes treatment.

Frequent monitoring of relevant laboratory parameters (e.g. International Normalized Ratio [INR] in patients taking warfarin, blood glucose levels in diabetic patients) or drug concentrations of concomitant medications such as CYP P450 substrates with a narrow therapeutic index (e.g. certain immunosuppressants) is recommended to ensure safe and effective use. Dose adjustments of concomitant medications may be necessary.

Table 6 provides the effect of MAVYRET on concentrations of coadministered drugs and the effect of coadministered drugs on glecaprevir and pibrentasvir [see Contraindications (4), Warnings and Precautions (5.3), and Clinical Pharmacology (12.3)]. All interaction studies were performed in adults.

Table 6. Potentially Significant Drug Interactions Identified in Drug Interaction Studies
Concomitant Drug Class: Drug Name | Effect on Concentration | Clinical Comments
Antiarrhythmics:
Digoxin | ↑ digoxin | Measure serum digoxin concentrations before initiating MAVYRET. Reduce digoxin concentrations by decreasing the dose by approximately 50% or by modifying the dosing frequency and continue monitoring.
Anticoagulants:
Dabigatran etexilate | ↑ dabigatran | If MAVYRET and dabigatran etexilate are coadministered, refer to the dabigatran etexilate prescribing information for dabigatran etexilate dose modifications in combination with P-gp inhibitors in the setting of renal impairment.
Anticonvulsants:
Carbamazepine | ↓ glecaprevir ↓ pibrentasvir | Coadministration may lead to reduced therapeutic effect of MAVYRET and is not recommended.
Antimycobacterials:
Rifampin | ↓ glecaprevir ↓ pibrentasvir | Coadministration is contraindicated because of potential loss of therapeutic effect [see Contraindications (4)].
Ethinyl Estradiol-Containing Products:
Ethinyl estradiol-containing medications such as combined oral contraceptives | ↔ glecaprevir ↔ pibrentasvir | MAVYRET may be used with products containing 20 mcg or less of ethinyl estradiol. Coadministration of MAVYRET with products containing more than 20 mcg of ethinyl estradiol may increase the risk of ALT elevations and is not recommended.
Herbal Products:
St. John’s wort (hypericum perforatum) | ↓ glecaprevir ↓ pibrentasvir | Coadministration may lead to reduced therapeutic effect of MAVYRET and is not recommended.
HIV-Antiviral Agents:
Atazanavir | ↑ glecaprevir ↑ pibrentasvir | Coadministration is contraindicated due to increased risk of ALT elevations [see Contraindications (4)].
Darunavir Lopinavir Ritonavir | ↑ glecaprevir ↑ pibrentasvir | Coadministration is not recommended.
Efavirenz | ↓ glecaprevir ↓ pibrentasvir | Coadministration may lead to reduced therapeutic effect of MAVYRET and is not recommended.
HMG-CoA Reductase Inhibitors:
Atorvastatin Lovastatin Simvastatin | ↑ atorvastatin ↑ lovastatin ↑ simvastatin | Coadministration may increase the concentration of atorvastatin, lovastatin, and simvastatin. Increased statin concentrations may increase the risk of myopathy, including rhabdomyolysis. Coadministration with these statins is not recommended.
Pravastatin | ↑ pravastatin | Coadministration may increase the concentration of pravastatin. Increased statin concentrations may increase the risk of myopathy, including rhabdomyolysis. Reduce pravastatin dose by 50% when coadministered with MAVYRET.
Rosuvastatin | ↑ rosuvastatin | Coadministration may significantly increase the concentration of rosuvastatin. Increased statin concentrations may increase the risk of myopathy, including rhabdomyolysis. Rosuvastatin may be administered with MAVYRET at a dose that does not exceed 10 mg.
Fluvastatin Pitavastatin | ↑ fluvastatin ↑ pitavastatin | Coadministration may increase the concentrations of fluvastatin and pitavastatin. Increased statin concentrations may increase the risk of myopathy, including rhabdomyolysis. Use the lowest approved dose of fluvastatin or pitavastatin. If higher doses are needed, use the lowest necessary statin dose based on a risk/benefit assessment.
Immunosuppressants:
Cyclosporine | ↑ glecaprevir ↑ pibrentasvir | MAVYRET is not recommended for use in patients requiring stable cyclosporine doses > 100 mg per day.
See Clinical Pharmacology, Tables 10 and 11.
↑= increase; ↓= decrease; ↔ = no effect

7.4 Medication-Assisted Treatment (MAT) for Opioid Use Disorder

No buprenorphine/naloxone or methadone dosage adjustment is required when used concomitantly with MAVYRET. There is insufficient information to make a recommendation regarding the concomitant use of naltrexone with MAVYRET.

7.5 Drugs with No Observed Clinically Significant Interactions with MAVYRET

No dose adjustment is required when MAVYRET is coadministered with the following medications: abacavir, amlodipine, caffeine, dextromethorphan, dolutegravir, elvitegravir/ cobicistat, emtricitabine, ethinyl estradiol of 20 mcg or less, felodipine, lamivudine, lamotrigine, losartan, midazolam, norethindrone or other progestin-only contraceptives, omeprazole, raltegravir, rilpivirine, sofosbuvir, tacrolimus, tenofovir alafenamide, tenofovir disoproxil fumarate, tolbutamide, and valsartan.

8 USE IN SPECIFIC POPULATIONS

8.1 Pregnancy

Risk Summary

No adequate human data are available to establish whether or not MAVYRET poses a risk to pregnancy outcomes. In animal reproduction studies, no adverse developmental effects were observed when the components of MAVYRET were administered separately during organogenesis at exposures up to 53 times (rats; glecaprevir) or 51 and 1.5 times (mice and rabbits, respectively; pibrentasvir) the human exposures at the recommended dose of MAVYRET (see Data). No definitive conclusions regarding potential developmental effects of glecaprevir could be made in rabbits, since the highest achieved glecaprevir exposure in this species was only 7% (0.07 times) of the human exposure at the recommended dose. There were no effects with either compound in rodent pre/post-natal developmental studies in which maternal systemic exposures (AUC) to glecaprevir and pibrentasvir were approximately 47 and 74 times, respectively, the exposure in humans at the recommended dose (see Data).

The background risk of major birth defects and miscarriage for the indicated population is unknown. In the U.S. general population, the estimated background risk of major birth defects and miscarriage in clinically recognized pregnancies is 2% to 4% and 15% to 20%, respectively.

Data

Glecaprevir

Glecaprevir was administered orally to pregnant rats (up to 120 mg/kg/day) and rabbits (up to 60 mg/kg/day) during the period of organogenesis (gestation days (GD) 6 to 18, and GD 7 to 19, respectively). No adverse embryo-fetal effects were observed in rats at dose levels up to 120 mg/kg/day (53 times the exposures in humans at the recommended human dose (RHD)). In rabbits, the highest glecaprevir exposure achieved was 7% (0.07 times) of the exposure in humans at RHD. As such, data in rabbits during organogenesis are not available for glecaprevir systemic exposures at or above the exposures in humans at the RHD.

In the pre/post-natal developmental study in rats, glecaprevir was administered orally (up to 120 mg/kg/day) from GD 6 to lactation day 20. No effects were observed at maternal exposures 47 times the exposures in humans at the RHD.

Pibrentasvir

Pibrentasvir was administered orally to pregnant mice and rabbits (up to 100 mg/kg/day) during the period of organogenesis (GD 6 to 15, and GD 7 to 19, respectively). No adverse embryo-fetal effects were observed at any studied dose level in either species. The systemic exposures at the highest doses were 51 times (mice) and 1.5 times (rabbits) the exposures in humans at the RHD.

In the pre/post-natal developmental study in mice, pibrentasvir was administered orally (up to 100 mg/kg/day) from GD 6 to lactation day 20. No effects were observed at maternal exposures approximately 74 times the exposures in humans at the RHD.

8.2 Lactation

Risk Summary

It is not known whether the components of MAVYRET are excreted in human breast milk, affect human milk production, or have effects on the breastfed infant. When administered to lactating rodents, the components of MAVYRET were present in milk, without effect on growth and development observed in the nursing pups (see Data).

The developmental and health benefits of breastfeeding should be considered along with the mother’s clinical need for MAVYRET and any potential adverse effects on the breastfed child from MAVYRET or from the underlying maternal condition.

Data

No significant effects of glecaprevir or pibrentasvir on growth and post-natal development were observed in nursing pups at the highest doses tested (120 mg/kg/day for glecaprevir and 100 mg/kg/day for pibrentasvir). Maternal systemic exposure (AUC) to glecaprevir and pibrentasvir was approximately 47 or 74 times the exposure in humans at the RHD. Systemic exposure in nursing pups on post-natal day 14 was approximately 0.6 to 2.2 % of the maternal exposure for glecaprevir and approximately one quarter to one third of the maternal exposure for pibrentasvir.

Glecaprevir or pibrentasvir was administered (single dose; 5 mg/kg oral) to lactating rats, 8 to 12 days post parturition. Glecaprevir in milk was 13 times lower than in plasma and pibrentasvir in milk was 1.5 times higher than in plasma. Parent drug (glecaprevir or pibrentasvir) represented the majority (>96%) of the total drug-related material in milk.

8.4 Pediatric Use

No dosage adjustment of MAVYRET is required in pediatric patients 12 years and older or weighing at least 45 kg. The recommended dosage of MAVYRET in pediatric patients 3 to less than 12 years of age is based on weight [see Dosage and Administration (2.2, 2.4), Clinical Pharmacology (12.3) and Clinical Studies (14.10)].

The safety, efficacy, and pharmacokinetics of MAVYRET in HCV GT1, 2, 3, or 4 infected pediatric patients 3 years and older is based on data from an open-label trial in 127 subjects with chronic HCV infection, without cirrhosis, and aged 3 years to less than 18 years who were either treatment-naïve (n=114) or treatment-experienced (n=13) and received MAVYRET for 8, 12 or 16 weeks (DORA-Part 1 and Part 2).

The adverse reactions observed in subjects 3 years to less than 18 years of age were consistent with those observed in clinical trials of MAVYRET in adults with chronic HCV infection with the exception of vomiting, rash and abdominal pain upper which were observed more frequently in pediatric subjects less than 12 years of age compared to adults [see Adverse Reactions (6.1)].

The efficacy results observed in this trial were consistent with those observed in clinical trials of MAVYRET in adults [see Clinical Studies (14.10)].

Use of MAVYRET in pediatric patients with acute HCV infection is supported by extrapolation of safety and efficacy data from adult patients with acute HCV infection and adult and pediatric patients with chronic HCV infection. It is expected that adult and pediatric patients with acute HCV infection have similar disease response to treatment. No clinically meaningful differences in MAVYRET exposures are expected among pediatric patients with acute HCV infection and pediatric patients with chronic HCV infection [see Clinical Pharmacology (12.3)].

In pediatric patients with cirrhosis, history of a kidney and/or liver transplant, or HCV GT5 or 6 infection, the safety and efficacy of MAVYRET are supported by the comparable glecaprevir and pibrentasvir exposures observed between pediatric subjects and adults [see Clinical Pharmacology (12.3)].

The safety and effectiveness of MAVYRET in children less than 3 years of age have not been studied.

8.5 Geriatric Use

In clinical trials of MAVYRET in subjects with chronic HCV infection, 328 subjects were age 65 years and over (14% of the total number of subjects in the Phase 2 and 3 clinical trials), and 47 (2%) subjects were age 75 and over. In a clinical trial of MAVYRET in subjects with acute HCV infection, 16 subjects were age 65 years and over (6%), and 1 (0.3%) subject was age 75 and over. No overall differences in safety or effectiveness were observed between these subjects and younger subjects, and other reported clinical experience has not identified differences in responses between the elderly and younger subjects. No dosage adjustment of MAVYRET is warranted in geriatric patients [see Clinical Pharmacology (12.3)].

8.6 Renal Impairment

No dosage adjustment of MAVYRET is required in patients with mild, moderate or severe renal impairment, including those on dialysis [see Clinical Pharmacology (12.3) and Clinical Studies (14.5)].

8.7 Hepatic Impairment

No dosage adjustment of MAVYRET is required in patients with mild hepatic impairment (Child-Pugh A). MAVYRET has not been evaluated and is contraindicated in HCV-infected patients with moderate or severe hepatic impairment (Child-Pugh B or Child-Pugh C) or those with any history of prior hepatic decompensation [see Contraindications (4)]. Postmarketing cases of hepatic decompensation/failure have been reported in these patients [see Warnings and Precautions (5.2)]. Higher exposures of both glecaprevir and pibrentasvir occur in subjects with severe hepatic impairment (Child-Pugh C) [see Clinical Pharmacology (12.3)].

8.8 People Who Inject Drugs (PWID) and those on Medication-Assisted Treatment (MAT) for Opioid Use Disorder

No dosage adjustment of MAVYRET is required in PWID or those who are on MAT for opioid use disorder. In clinical trials of MAVYRET, the safety and efficacy were similar between subjects who self-identified as current/recent PWID, those who were former PWID, and those who did not report history of injection drug use. The safety and efficacy of MAVYRET were also similar between subjects who reported concomitant MAT for opioid use disorder and those who did not report concomitant MAT [see Adverse Reactions (6.1), Drug Interactions (7.4) and Clinical Studies (14.9)].

10 OVERDOSAGE

In case of overdose, the patient should be monitored for any signs and symptoms of toxicities. Appropriate symptomatic treatment should be instituted immediately. Glecaprevir and pibrentasvir are not significantly removed by hemodialysis.

11 DESCRIPTION

MAVYRET contains glecaprevir, a HCV NS3/4A PI, and pibrentasvir a HCV NS5A inhibitor. MAVYRET is available as a fixed dose combination tablet or coated pellets in unit-dose packets for oral administration.

Glecaprevir/Pibrentasvir Film-Coated Immediate Release Tablets

Each tablet contains 100 mg of glecaprevir and 40 mg of pibrentasvir. Glecaprevir and pibrentasvir are presented as a co-formulated, fixed-dose combination, immediate release bilayer tablet.

The tablet contains the following inactive ingredients: colloidal silicon dioxide, copovidone (type K 28), croscarmellose sodium, hypromellose 2910, iron oxide red, lactose monohydrate, polyethylene glycol 3350, propylene glycol monocaprylate (type II), sodium stearyl fumarate, titanium dioxide, and vitamin E (tocopherol) polyethylene glycol succinate.

The tablets do not contain gluten.

Glecaprevir/Pibrentasvir Coated Oral Pellets

MAVYRET oral pellets are small, pink and yellow and supplied in unit-dose packets for oral administration. Each unit-dose of MAVYRET oral pellets in packets contains 50 mg glecaprevir and 20 mg pibrentasvir and the following inactive ingredients: colloidal silicon dioxide, copovidone (type K 28), croscarmellose sodium, hypromellose 2910, iron oxide red, iron oxide yellow, lactose monohydrate, polyethylene glycol/macrogol 3350, propylene glycol monocaprylate (type II), sodium stearyl fumarate, titanium dioxide, vitamin E (tocopherol) polyethylene glycol succinate.

The oral pellets do not contain gluten.

Glecaprevir drug substance:

The chemical name of glecaprevir is (3aR,7S,10S,12R,21E,24aR)-7-tert-butyl-N-{(1R,2R)-2-(difluoromethyl)-1-[(1-methylcyclopropane-1-sulfonyl)carbamoyl]cyclopropyl}-20,20-difluoro-5,8-dioxo-2,3,3a,5,6,7,8,11,12,20,23,24a-dodecahydro-1H,10H-9,12-methanocyclopenta[18,19][1,10,17,3,6]trioxadiazacyclononadecino[11,12-b]quinoxaline-10-carboxamide hydrate.

The molecular formula is C38H46F4N6O9S (anhydrate) and the molecular weight for the drug substance is 838.87 g/mol (anhydrate). The strength of glecaprevir is based on anhydrous glecaprevir. Glecaprevir is a white to off-white crystalline powder with a solubility of less than 0.1 to 0.3 mg/mL across a pH range of 2–7 at 37°C and is practically insoluble in water, but is sparingly soluble in ethanol. Glecaprevir has the following molecular structure:

Pibrentasvir drug substance:

The chemical name of pibrentasvir is Methyl {(2S,3R)-1-[(2S)-2-{5-[(2R,5R)-1-{3,5-difluoro-4-[4-(4-fluorophenyl)piperidin-1-yl]phenyl}-5-(6-fluoro-2-{(2S)-1-[N-(methoxycarbonyl)-O-methyl-L-threonyl]pyrrolidin-2-yl}-1H-benzimidazol-5-yl)pyrrolidin-2-yl]-6-fluoro-1H-benzimidazol-2-yl}pyrrolidin-1-yl]-3-methoxy-1-oxobutan-2-yl}carbamate.

The molecular formula is C57H65F5N10O8 and the molecular weight for the drug substance is 1113.18 g/mol. Pibrentasvir is a white to off-white to light yellow crystalline powder with a solubility of less than 0.1 mg/mL across a pH range of 1–7 at 37°C and is practically insoluble in water, but is freely soluble in ethanol. Pibrentasvir has the following molecular structure:

12 CLINICAL PHARMACOLOGY

12.1 Mechanism of Action

Mechanism of Action

MAVYRET is a fixed-dose combination of glecaprevir and pibrentasvir, which are direct-acting antiviral agents against the hepatitis C virus [see Microbiology (12.4)].

12.2 Pharmacodynamics

Cardiac Electrophysiology

The effect of doses up to glecaprevir 600 mg (2 times the recommended dosage) with doses up to pibrentasvir 240 mg (2 times the recommended dosage) on QTc interval was evaluated in an active-controlled (moxifloxacin 400 mg) thorough QT study. At 20-fold of glecaprevir and 5-fold of pibrentasvir therapeutic concentrations, the glecaprevir and pibrentasvir combination does not prolong the QTc interval to any clinically relevant extent.

12.3 Pharmacokinetics

The pharmacokinetic properties of the components of MAVYRET in healthy subjects are provided in Table 7. The steady-state pharmacokinetic parameters of glecaprevir and pibrentasvir in subjects with chronic HCV infection without cirrhosis are provided in Table 8. For pellets relative to tablets in healthy adult subjects under non-fasting conditions, geometric mean ratios (GMRs) of glecaprevir and pibrentasvir Cmax were 0.664 and 1.137, AUCinf were 0.795 and 1.219, and C24 (concentrations at 24 hours post-dose) were 0.917 and 1.174. These differences were not considered clinically significant.

Table 7. Pharmacokinetic Properties of the Components of MAVYRET in Healthy Subjects
 | Glecaprevir | Pibrentasvir
Absorption
Tmax (h)a of tablets | 5.0 | 5.0
Tmax (h)a of oral pellets | 3.0 | 5.0
Effect of meal (relative to fasting)b on tablets | ↑ 83-163% | ↑ 40-53%
Effect of meal (relative to fasting)b on oral pellets | ↑ 131-167% | ↑ 56-114%
Distribution
% Bound to human plasma proteins | 97.5 | >99.9
Blood-to-plasma ratio | 0.57 | 0.62
Elimination
t1/2 (h) | 6 | 13
Metabolism | secondary, | None
 | CYP3A
Major route of excretion | biliary-fecal | biliary-fecal
% of dose excreted in urinec | 0.7 | 0
% of dose excreted in fecesc | 92.1 | 96.6
a. Median Tmax following single doses of glecaprevir and pibrentasvir in healthy subjects.
b. Mean systemic exposures with low/moderate to high fat meals.
c. Single dose administration of radiolabeled glecaprevir or pibrentasvir in mass balance studies.

Table 8. Steady-State Pharmacokinetic Parameters of Glecaprevir and Pibrentasvir Following Administration of MAVYRET in Subjects with Chronic HCV Infection without Cirrhosis
Pharmacokinetic Parameter | Glecaprevirb | Pibrentasvirc
Cmax (ng/mL)a | 597 (114) | 110 (49)
AUC24,ss (ng•h/mL)a | 4800 (122) | 1430 (57)
Ctrough,ss (ng/mL)a | 13.0 (334) | 18.9 (92)
a Geometric mean (%CV) of individual-estimated Cmax, AUC24,ss and Ctrough,ss values
b Relative to healthy subjects, glecaprevir Cmax was 51% lower, AUC24,ss was similar (10% difference), and Ctrough,ss was 157% higher in subjects without cirrhosis with chronic HCV infection
c Relative to healthy subjects, pibrentasvir Cmax was 63% lower, AUC24,ss was 34% lower, and Ctrough,ss was 37% lower in subjects without cirrhosis with chronic HCV infection

No clinically meaningful differences in glecaprevir and pibrentasvir exposures are expected among adult patients with acute HCV infection and adult patients with chronic HCV infection.

Specific Populations

Pediatric Patients

The pharmacokinetics of glecaprevir and pibrentasvir were determined in pediatric subjects with chronic HCV infection who were 3 years of age and older receiving a daily dose of MAVYRET as described below in Table 9. GMRs of glecaprevir and pibrentasvir Cmax and AUC24 in pediatrics vs. adults with chronic HCV infection ranged from 1.58-2.68 and 0.965-1.64, respectively. GMRs of glecaprevir Ctrough ranged from 0.292-0.954 and GMRs of pibrentasvir Ctrough ranged from 0.794-1.93. All pediatric glecaprevir and pibrentasvir PK parameter values fell within the range observed in adult subjects. These differences were not considered clinically significant.

No clinically meaningful differences in glecaprevir and pibrentasvir exposures are expected among pediatric patients with acute HCV infection and pediatric patients with chronic HCV infection.

The pharmacokinetics of glecaprevir and pibrentasvir have not been established in children less than 3 years of age.

Table 9. Pharmacokinetic Parameters of Glecaprevir (GLE) and Pibrentasvir (PIB) in Pediatric Subjects with Chronic HCV Infection
Age and Weight (kg) | N | Total Daily Dose of GLE/PIB (mg) | PK Parameter | Geometric Mean (%CV)
 |  |  |  | GLE | PIB
12 to < 18 years, ≥ 45 kg | 14 | 300/120 | AUC24 (ng•h/mL) | 4790 (72) | 1380 (40)
 |  |  | Cmax (ng/mL) | 1040 (86) | 174 (36)
 |  |  | Ctrough (ng/mL) | 3.79 (82) | 15.0 (61)
9 to < 12 years, 30 to < 45 kg | 13 | 250/100 | AUC24 (ng•h/mL) | 7870 (209) | 2200 (99)
 |  |  | Cmax (ng/mL) | 1370 (169) | 225 (72)
 |  |  | Ctrough (ng/mL) | 12.4 (856) | 36.5 (164)
6 to < 9 years, 20 to < 30 kg | 13 | 200/80 | AUC24 (ng•h/mL) | 6860 (142) | 1640 (63)
 |  |  | Cmax (ng/mL) | 1600 (155) | 197 (52)
 |  |  | Ctrough (ng/mL) | 7.44 (383) | 19.4 (103)
3 to < 6 years, 12 to < 20 kg | 12 | 150/60 | AUC24 (ng•h/mL) | 7520 (205) | 1790 (58)
 |  |  | Cmax (ng/mL) | 1530 (280) | 233 (48)
 |  |  | Ctrough (ng/mL) | 6.58 (318) | 17.9 (119)

Subjects with Renal Impairment

Glecaprevir and pibrentasvir AUC were increased ≤ 56% in non-HCV infected subjects with mild, moderate, severe, or end-stage renal impairment (GFR estimated using Modification of Diet in Renal Disease) not on dialysis compared to subjects with normal renal function. Glecaprevir and pibrentasvir AUC were similar with and without dialysis (≤ 18% difference) in dialysis-dependent non-HCV infected subjects. In subjects with chronic HCV infection, 86% higher glecaprevir and 54% higher pibrentasvir AUC were observed for subjects with end stage renal disease, with or without dialysis, compared to subjects with normal renal function.

Subjects with Hepatic Impairment

Following administration of MAVYRET in subjects with chronic HCV infection and compensated cirrhosis (Child-Pugh A), exposure of glecaprevir was approximately 2-fold and pibrentasvir exposure was similar to non-cirrhotic subjects with chronic HCV infection.

At the clinical dose, compared to non-HCV infected subjects with normal hepatic function, glecaprevir AUC was 100% higher in Child-Pugh B subjects, and increased 11-fold in Child-Pugh C subjects. Pibrentasvir AUC was 26% higher in Child-Pugh B subjects, and 114% higher in Child-Pugh C subjects.

Age/Gender/Race/Body Weight

No clinically significant differences in the pharmacokinetics of glecaprevir or pibrentasvir were observed based on age (12-88 years), sex, race/ethnicity or body weight (45 kg or greater). Patients under the age of 12 and weighing less than 45 kg are dosed based on body weight [see Dosage and Administration (2.4)].

Drug Interaction Studies

Drug interaction studies were performed with glecaprevir/pibrentasvir and other drugs that are likely to be coadministered and with drugs commonly used as probes for pharmacokinetic interactions. Tables 10 and 11 summarize the pharmacokinetic effects when glecaprevir/pibrentasvir was coadministered with other drugs which showed potentially clinically relevant changes. Significant interactions are not expected when MAVYRET is coadministered with substrates of CYP3A, CYP1A2, CYP2C9, CYP2C19, CYP2D6, UGT1A1, or UGT1A4.

Table 10. Drug Interactions: Changes in Pharmacokinetic Parameters of Glecaprevir (GLE) or Pibrentasvir (PIB) in the Presence of Coadministered Drug
Co- administered Drug | Regimen of Co- administered Drug (mg) | Regimen of GLE/PIB (mg) | N | DAA | Central Value Ratio (90% CI)
 |  |  |  |  | Cmax | AUC | Cmin
Atazanavir + ritonavir | 300 + 100 once daily | 300/120 once dailya | 12 | GLE | ≥4.06 (3.15, 5.23) | ≥6.53 (5.24, 8.14) | ≥14.3 (9.85, 20.7)
 |  |  |  | PIB | ≥1.29 (1.15, 1.45) | ≥1.64 (1.48, 1.82) | ≥2.29 (1.95, 2.68)
Carbamazepine | 200 twice daily | 300/120 single dose | 10 | GLE | 0.33 (0.27, 0.41) | 0.34 (0.28, 0.40) | --
 |  |  |  | PIB | 0.50 (0.42, 0.59) | 0.49 (0.43, 0.55) | --
Cyclosporine | 100 single dose | 300/120 once daily | 12 | GLEb | 1.30 (0.95, 1.78) | 1.37 (1.13, 1.66) | 1.34 (1.12, 1.60)
 |  |  |  | PIB | ↔ | ↔ | 1.26 (1.15, 1.37)
 | 400 single dose | 300/120 single dose | 11 | GLE | 4.51 (3.63, 6.05) | 5.08 (4.11, 6.29) | --
 |  |  |  | PIB | ↔ | 1.93 (1.78, 2.09) | --
Darunavir + ritonavir | 800 + 100 once daily | 300/120 once daily | 8 | GLE | 3.09 (2.26, 4.20) | 4.97 (3.62, 6.84) | 8.24 (4.40, 15.4)
 |  |  |  | PIB | ↔ | ↔ | 1.66 (1.25, 2.21)
Elvitegravir/ cobicistat/ emtricitabine/ tenofovir alafenamide | 150/150/ 200/10 once daily | 300/120 once daily | 11 | GLE | 2.50 (2.08, 3.00) | 3.05 (2.55, 3.64) | 4.58 (3.15,6.65)
 |  |  |  | PIB | ↔ | 1.57 (1.39, 1.76) | 1.89 (1.63, 2.19)
Omeprazole | 20 once daily | 300/120 single dose | 9 | GLE | 0.78 (0.60, 1.00) | 0.71 (0.58, 0.86) | --
 |  |  |  | PIB | ↔ | ↔ | --
 | 40 once daily (1 hour before GLE/PIB) | 300/120 single dose | 12 | GLE | 0.36 (0.21, 0.59) | 0.49 (0.35, 0.68) | --
 |  |  |  | PIB | ↔ | ↔ | --
Rifampin | 600 (first dose) | 300/120 single dose | 12 | GLE | 6.52 (5.06, 8.41) | 8.55 (7.01, 10.4) | --
 |  |  |  | PIB | ↔ | ↔ | --
 | 600 once daily | 300/120 single dosec | 12 | GLE | 0.14 (0.11, 0.19) | 0.12 (0.09, 0.15) | --
 |  |  |  | PIB | 0.17 (0.14, 0.20) | 0.13 (0.11, 0.15) | --
Lopinavir/ ritonavir | 400/100 twice daily | 300/120 once daily | 9 | GLE | 2.55 (1.84, 3.52) | 4.38 (3.02, 6.36) | 18.6 (10.4, 33.5)
 |  |  |  | PIB | 1.40 (1.17, 1.67) | 2.46 (2.07, 2.92) | 5.24 (4.18, 6.58)
↔ = No change (central value ratio 0.80 to 1.25)
a. Effect of atazanavir and ritonavir on the first dose of glecaprevir and pibrentasvir is reported.
b. HCV-infected transplant recipients who received cyclosporine dose of 100 mg or less per day had mean glecaprevir exposures 2.4-fold of those not receiving cyclosporine.
c. Effect of rifampin on glecaprevir and pibrentasvir 24 hours after final rifampin dose.

Table 11. Drug Interactions: Changes in Pharmacokinetic Parameters for Coadministered Drug in the Presence of Combination of Glecaprevir/Pibrentasvir (GLE/PIB)
Co- administered Drug | Regimen of Co- administered Drug (mg) | Regimen of GLE/PIB (mg) | N | Central Value Ratio (90% CI)
 |  |  |  | Cmax | AUC | Cmin
Abacavir | ABC/DTG/3TC 600/50/300 once daily | 300/120 once daily | 12 | ↔ | ↔ | 1.31 (1.05, 1.63)
Atorvastatin | 10 once daily | 400/120 once daily | 11 | 22.0 (16.4, 29.6) | 8.28 (6.06, 11.3) | --
Caffeine | 100 single dose | 300/120 once daily | 12 | ↔ | 1.35 (1.23, 1.48) | --
Dabigatran | Dabigatran etexilate 150 single dose | 300/120 once daily | 11 | 2.05 (1.72, 2.44) | 2.38 (2.11, 2.70) | --
Darunavir | DRV + RTV 800 + 100 once daily | 300/120 once daily | 12 | 1.30 (1.21, 1.40) | 1.29 (1.18, 1.42) | ↔
Ritonavir |  |  |  | 2.03 (1.78, 2.32) | 1.87 (1.74, 2.02) | ↔
Dextro- methorphan | Dextromethorphan hydrobromide 30 single dose | 300/120 once daily | 12 | 0.70 (0.61, 0.81) | 0.75 (0.66, 0.85) | --
Digoxin | 0.5 single dose | 400/120 once daily | 12 | 1.72 (1.45, 2.04) | 1.48 (1.40, 1.57) | --
Ethinyl estradiol (EE) | EE/ Norgestimate 35 µg/250 µg once daily | 300/120 once daily | 11 | 1.31 (1.24, 1.38) | 1.28 (1.23, 1.32) | 1.38 (1.25, 1.52)
Norgestrel |  |  |  | 1.54 (1.34, 1.76) | 1.63 (1.50, 1.76) | 1.75 (1.62, 1.89)
Norgestromin |  |  |  | ↔ | 1.44 (1.34, 1.54) | 1.45 (1.33, 1.58)
Ethinyl estradiol | EE/ Levonorgestrel 20 µg/100 µg once daily | 300/120 once daily | 12 | 1.30 (1.18, 1.44) | 1.40 (1.33, 1.48) | 1.56 (1.41, 1.72)
Norgestrel |  |  |  | 1.37 (1.23, 1.52) | 1.68 (1.57, 1.80) | 1.77 (1.58, 1.98)
Elvitegravir | EVG/COBI/FTC/ TAF 150/ 150/200/10 once daily | 300/120 once daily | 12 | 1.36 (1.24, 1.49) | 1.47 (1.37, 1.57) | 1.71 (1.50, 1.95)
Tenofovir |  |  |  | ↔ | ↔ | ↔
Felodipine | 2.5 single dose | 300/120 once daily | 11 | 1.31 (1.05, 1.62) | 1.31 (1.08, 1.58) | --
Losartan | 50 single dose | 300/120 once daily | 12 | 2.51 (2.00, 3.15) | 1.56 (1.28, 1.89) | --
Losartan carboxylic acid |  |  |  | 2.18 (1.88, 2.53) | ↔ | --
Lovastatin | Lovastatin 10 once daily | 300/120 once daily | 12 | ↔ | 1.70 (1.40, 2.06) | --
Lovastatin acid |  |  |  | 5.73 (4.65, 7.07) | 4.10 (3.45, 4.87) | --
Midazolam | 1 single dose | 300/120 once daily | 12 | ↔ | 1.27 (1.11, 1.45) | --
Omeprazole | 20 single dose | 300/120 once daily | 12 | 0.57 (0.43, 0.75) | 0.79 (0.70, 0.90) | --
Pravastatin | 10 once daily | 400/120 once daily | 12 | 2.23 (1.87, 2.65) | 2.30 (1.91, 2.76) | --
Raltegravir | 400 twice daily | 300/120 once daily | 12 | 1.34 (0.89, 1.98) | 1.47 (1.15, 1.87) | 2.64 (1.42, 4.91)
Rilpivirine | 25 once daily | 300/120 once daily | 12 | 2.05 (1.73, 2.43) | 1.84 (1.72, 1.98) | 1.77 (1.59, 1.96)
Rosuvastatin | 5 once daily | 400/120 once daily | 11 | 5.62 (4.80, 6.59) | 2.15 (1.88, 2.46) | --
Simvastatin | Simvastatin 5 once daily | 300/120 once daily | 12 | 1.99 (1.60, 2.48) | 2.32 (1.93, 2.79) | --
Simvastatin acid |  |  |  | 10.7 (7.88, 14.6) | 4.48 (3.11, 6.46) | --
Sofosbuvir | Sofosbuvir 400 once daily | 400/120 once daily | 8 | 1.66 (1.23, 1.22) | 2.25 (1.86, 2.72) | --
GS-331007 |  |  |  | ↔ | ↔ | 1.85 (1.67, 2.04)
Tacrolimus | 1 single dose | 300/120 once daily | 10 | 1.50 (1.24, 1.82) | 1.45 (1.24, 1.70) | --
Tenofovir | EFV/FTC/TDF 300/200/300 once daily | 300/120 once daily | 12 | ↔ | 1.29 (1.23, 1.35) | 1.38 (1.31, 1.46)
Valsartan | 80 single dose | 300/120 once daily | 12 | 1.36 (1.17, 1.58) | 1.31 (1.16, 1.49) | --
↔ = No change (central value ratio 0.80 to 1.25)
3TC – lamivudine; ABC – abacavir; COBI – cobicistat; DRV – darunavir; DTG – dolutegravir; EFV – efavirenz; EVG – elvitegravir; FTC – emtricitabine; RTV – ritonavir; TAF – tenofovir alafenamide; TDF – tenofovir disoproxil fumarate

12.4 Microbiology

Mechanism of Action

Glecaprevir

Glecaprevir is an inhibitor of the HCV NS3/4A protease, which is necessary for the proteolytic cleavage of the HCV encoded polyprotein (into mature forms of the NS3, NS4A, NS4B, NS5A, and NS5B proteins) and is essential for viral replication. In a biochemical assay, glecaprevir inhibited the proteolytic activity of recombinant NS3/4A enzymes from clinical isolates of HCV genotypes 1a, 1b, 2a, 2b, 3a, 4a, 5a, and 6a with IC50 values ranging from 3.5 to 11.3 nM.

Pibrentasvir

Pibrentasvir is an inhibitor of HCV NS5A, which is essential for viral RNA replication and virion assembly. The mechanism of action of pibrentasvir has been characterized based on cell culture antiviral activity and drug resistance mapping studies.

Antiviral Activity

In HCV replicon assays, glecaprevir had median EC50 values of 0.08-4.6 nM against laboratory and clinical isolates from subtypes 1a, 1b, 2a, 2b, 3a, 3b, 4a, 4d, 5a, and 6a. Pibrentasvir had median EC50 values of 0.5-15.6 pM against laboratory and clinical isolates from subtypes 1a, 1b, 2a, 2b, 3a, 3b, 4a, 4b, 4d, 5a, 6a, 6e and 6p.

Combination Antiviral Activity

Evaluation of combination of glecaprevir and pibrentasvir showed no antagonism in antiviral activity in HCV genotype 1 replicon cell culture assays.

Resistance

In Cell Culture

Selection of HCV genotype 1a, 1b, 2a, 3a, 4a or 6a replicons for reduced susceptibility to glecaprevir resulted in the emergence of amino acid substitutions most commonly at NS3 positions A156 or D/Q168. Individual substitutions at NS3 amino acid position A156 introduced into HCV replicons by site-directed mutagenesis generally caused the greatest reductions (>100-fold) in susceptibility to glecaprevir. Individual substitutions at NS3 position D/Q168 had varying effects on glecaprevir susceptibility depending on HCV genotype/subtype and specific amino acid change, with the greatest reductions (>30-fold) observed in genotypes 1a (D168F/Y), 3a (Q168R) and 6a (D168A/G/H/V/Y). Combinations of NS3 Y56H plus D/Q168 substitutions resulted in greater reductions in glecaprevir susceptibility. An NS3 Q80R substitution in genotype 3a caused a 21-fold reduction in glecaprevir susceptibility, while Q80 substitutions in genotypes 1a and 1b (including genotype 1a Q80K) did not reduce glecaprevir susceptibility. Individual amino acid substitutions associated with resistance to other HCV protease inhibitors at positions 36, 43, 54, 55, 56, 155, 166, or 170 in NS3 generally did not reduce susceptibility to glecaprevir.

Selection of HCV genotype 1a, 2a or 3a replicons for reduced susceptibility to pibrentasvir resulted in the emergence of amino acid substitutions at known NS5A inhibitor resistance-associated positions, including Q30D/deletion, Y93D/H/N or H58D +Y93H in genotype 1a replicons, F28S + M31I or P29S + K30G in genotype 2a replicons, and Y93H in genotype 3a replicons. The majority of individual amino acid substitutions associated with resistance to other HCV NS5A inhibitors at positions 24, 28, 30, 31, 58, 92, or 93 in NS5A did not reduce susceptibility to pibrentasvir. Individual NS5A amino acid substitutions that reduced susceptibility to pibrentasvir include M28G or Q30D in a genotype 1a replicon (244- and 94-fold, respectively), and P32-deletion in a genotype 1b replicon (1,036-fold). Some combinations of two or more NS5A inhibitor resistance-associated amino acid substitutions may result in greater reductions in pibrentasvir susceptibility. In a genotype 3b replicon, the presence of naturally occurring polymorphisms K30 and M31 in NS5A reduced susceptibility to pibrentasvir by 24-fold relative to the activity of pibrentasvir in a genotype 3a replicon. Introduction of an NS5A Y93H substitution into a genotype 3b replicon further reduced susceptibility to pibrentasvir by 6336-fold.

In Clinical Studies of Subjects with Chronic HCV Infection

Studies in Treatment-Naïve and (peg)Interferon, Ribavirin and/or Sofosbuvir Treatment-Experienced Subjects with or without Cirrhosis

In pooled analyses of NS3/4A PI- and NS5A inhibitor-naïve subjects who received MAVYRET for 8, 12, or 16 weeks in the registrational Phase 2 and 3 clinical studies (including EXPEDITION-2 and MAGELLAN-2), treatment-emergent resistance analyses were conducted for 24 subjects who experienced virologic failure (2 with genotype 1, 2 with genotype 2, 20 with genotype 3 infection). No subjects with HCV genotype 4, 5 or 6 infection experienced virologic failure.

Among the two genotype 1-infected subjects who experienced virologic failure, both subjects had a subtype 1a infection. One subject had treatment-emergent substitutions A156V in NS3, and Q30R, L31M and H58D in NS5A (Q30R and L31M were also detected at a low frequency at baseline). One subject had treatment-emergent Q30R and H58D (while Y93N was present at baseline and post-treatment) in NS5A.

Among the two genotype 2-infected subjects who experienced virologic failure, both subjects had a subtype 2a infection, and no treatment-emergent substitutions were observed in NS3 or NS5A.

Among the 20 genotype 3-infected subjects who experienced virologic failure, treatment-emergent NS3 substitutions Y56H/N, Q80K/R, A156G, or Q168L/R were observed in 13 subjects. A166S or Q168R were present at baseline and post-treatment in 5 subjects. Treatment-emergent NS5A substitutions S24F, M28G/K, A30G/K, L31F, P58T, or Y93H were observed in 17 subjects, and 14 subjects had A30K (n=9) or Y93H (n=6) at baseline and post-treatment.

Studies in Subjects with or without Cirrhosis Who Were Treatment-Experienced to NS3/4A Protease and/or NS5A Inhibitors

Treatment-emergent resistance analyses were conducted for 11 HCV genotype 1-infected subjects (10 genotype 1a, 1 genotype 1b) with prior NS3/4A PI or NS5A inhibitor treatment experience who experienced virologic failure with MAVYRET with or without ribavirin in the MAGELLAN-1 study. Treatment-emergent NS3 substitutions V36A/M, Y56H, R155K/T, A156G/T/V, or D168A/T were observed in 73% (8/11) of subjects. Nine of 10 subjects (90%, not including one subject missing NS5A data at failure) had treatment-emergent NS5A substitutions M28A/G (or L28M for genotype 1b), P29Q/R, Q30K/R, H58D or Y93H/N. All 11 subjects also had NS5A inhibitor resistance-associated substitutions detected at baseline, and 7/11 had NS3 PI resistance-associated substitutions detected at baseline (see Cross-Resistance for the effect of baseline resistance-associated substitutions on treatment response for NS3/4A PI or NS5A inhibitor treatment-experienced patients).

Effect of Baseline HCV Amino Acid Polymorphisms on Treatment Response (NS3/4A PI- and NS5A Inhibitor-Naïve Subjects)

A pooled analysis of NS3/4A PI- and NS5A inhibitor-naïve subjects with chronic HCV infection who received MAVYRET in the Phase 2 and Phase 3 clinical studies was conducted to identify the HCV subtypes represented and explore the association between baseline amino acid polymorphisms and treatment outcome. Baseline polymorphisms relative to a subtype-specific reference sequence at resistance-associated amino acid positions 155, 156, and 168 in NS3, and 24, 28, 30, 31, 58, 92, and 93 in NS5A were evaluated at a 15% detection threshold by next-generation sequencing. Among subjects who received MAVYRET for 8-, 12-, or 16 weeks, baseline polymorphisms in NS3 were detected in 1% (9/845), 1% (3/398), 2% (10/613), 1% (2/164), 42% (13/31), and 3% (1/34) of subjects with HCV genotype 1, 2, 3, 4, 5, and 6 infection, respectively. No baseline polymorphisms were detected at NS3 amino acid position 156 across all genotypes. Baseline polymorphisms in NS5A were detected in 27% (225/841), 80% (331/415), 22% (136/615), 50% (80/161), 13% (4/31), and 54% (20/37) of subjects with HCV genotype 1, 2, 3, 4, 5, and 6 infection, respectively.

Genotype 1, 2, 4, 5, and 6: Baseline HCV polymorphisms in genotypes 1, 2, 4, 5 and 6 had no impact on treatment outcome.

Genotype 3: In registrational trials, HCV subtype 3a was the predominant genotype 3 subtype overall and was detected in >99% of U.S. genotype 3-infected subjects. Among treatment-naïve, genotype 3a-infected subjects without cirrhosis who received MAVYRET for 8 weeks, an NS5A A30K polymorphism was detected in 10% (18/179) of subjects, of whom 78% (14/18) achieved SVR12. Limited data are available to characterize the impact of the A30K polymorphism in genotype 3a-infected subjects with cirrhosis (n=3 who received MAVYRET for 8 weeks, all achieved SVR12) or prior treatment experience (n=1 who received MAVYRET for 16 weeks, relapse). In the pooled Phase 2 and Phase 3 trials, including post-registrational trials EXPEDITION-8, VOYAGE-1 and VOYAGE-2, 94% (15/16) of genotype 3a-infected subjects with Y93H in NS5A at baseline who received the recommended MAVYRET regimens achieved SVR12. In MAGELLAN-2 (post-transplant subjects), SVR12 was achieved in 2 of 3 (67%) genotype 3-infected subjects with the NS5A Y93H baseline polymorphism. In the VOYAGE-1 and VOYAGE-2 trials conducted in China, Singapore, and South Korea, 50% (20/40) of genotype 3-infected subjects had subtype 3b, of whom 14 (70%) achieved SVR12 with MAVYRET durations of 8, 12 or 16 weeks [see Clinical Studies (14.4)]. The naturally occurring NS5A K30 and M31 polymorphisms were detected in 95% (19/20) and 100% (20/20) of genotype 3b-infected subjects.

Subjects with acute HCV infection: Analyses of baseline HCV polymorphisms were conducted for acute HCV-infected subjects who received MAVYRET for 8 weeks in the Phase 3b clinical study (M20-350), and the analyses considered the same NS3 and NS5A resistance-associated positions as described above for subjects with chronic HCV infection. Baseline HCV polymorphisms in NS3 or NS5A were detected in <1% (1/170) or 25% (46/181) of subjects, respectively, and had no impact on treatment outcome; no subjects experienced virologic failure.

Cross-resistance

Based on resistance patterns observed in cell culture replicon studies and chronic HCV-infected subjects, cross-resistance is possible between glecaprevir and other HCV NS3/4A PIs, and between pibrentasvir and other HCV NS5A inhibitors. Cross-resistance is not expected between MAVYRET and sofosbuvir, (peg)interferon or ribavirin.

In the MAGELLAN-1 study, HCV genotype 1-infected subjects who had failed prior treatment with NS3/4A protease and/or NS5A inhibitors were treated with MAVYRET for 12 or 16 weeks. Baseline sequences were analyzed by next generation sequencing at a 15% detection threshold.

Among 23 NS3/4A PI-experienced/NS5A inhibitor-naïve subjects who received MAVYRET for 12 weeks in MAGELLAN-1 (excluding 2 non-virologic failure subjects), 2 subjects each had baseline NS3 R155K or D168E/V substitutions; all 23 subjects achieved SVR12.

Among NS5A inhibitor-experienced/PI-naïve subjects who received MAVYRET for 16 weeks, baseline NS5A resistance-associated substitutions [R30Q (n=1), Y93H/N (n=5), M28A+Q30R (n=1), Q30H+Y93H (n=1), Q30R+L31M (n=2), L31M+H58P (n=1)], were detected in 73% (11/15) of subjects with available data, of whom 91% (10/11) achieved SVR12. The non-SVR12 subject experienced on-treatment virologic failure and had a genotype 1a infection with baseline NS5A Q30R and L31M substitutions.

Persistence of Resistance-Associated Substitutions

Certain NS5A inhibitor resistance-associated substitutions have been found to persist for >1 year in some patients. Viral populations with NS3 resistance-associated substitutions have been found to decline in some patients through post-treatment weeks 24 and 48. The long-term clinical impact of the emergence or persistence of virus containing glecaprevir or pibrentasvir resistance-associated substitutions is unknown.

13 NONCLINICAL TOXICOLOGY

13.1 Carcinogenesis, Mutagenesis, Impairment of Fertility

Carcinogenesis and Mutagenesis

Glecaprevir and pibrentasvir were not genotoxic in a battery of in vitro or in vivo assays, including bacterial mutagenicity, chromosome aberration using human peripheral blood lymphocytes and in vivo rodent micronucleus assays.

Carcinogenicity studies with glecaprevir and pibrentasvir have not been conducted.

Impairment of Fertility

No effects on mating, female or male fertility, or early embryonic development were observed in rodents at up to the highest dose tested. Systemic exposures (AUC) to glecaprevir and pibrentasvir were approximately 63 and 102 times higher, respectively, than the exposure in humans at the recommended dose.

14 CLINICAL STUDIES

14.1 Description of Clinical Trials

Table 12 summarizes the clinical trials conducted to support the effectiveness of MAVYRET in subjects with HCV genotype 1, 2, 3, 4, 5 or 6 infection and compensated liver disease (including Child-Pugh A cirrhosis) according to treatment history and cirrhosis status.

Table 12. Clinical Trials Conducted with MAVYRET in Subjects with HCV Genotype 1, 2, 3, 4, 5 or 6 Infection and Compensated Liver Disease
Genotype (GT) | Clinical Trial (NCT Number) |  | Treatment Duration*
Clinical Trials of Chronic HCV Infection
TN and PRS-TE Subjects without Cirrhosis
GT1** | ENDURANCE-1 (NCT02604017) |  | MAVYRET for 8 (n=351) or 12 weeks (n=352)
GT2 | SURVEYOR-2 (NCT02243293) |  | MAVYRET for 8 weeks (n=197)
GT3 | ENDURANCE-3 (NCT02640157) |  | MAVYRET for 8 (n=157) or 12 weeks (n=233) sofosbuvir + daclatasvir for 12 weeks (n=115)
 | SURVEYOR-2 |  | MAVYRET for 16 (PRS-TE only) weeks (n=22)
GT4, 5, 6 | ENDURANCE-5,6 (NCT02966795) |  | MAVYRET for 8 weeks (GT5 n=20; GT6 n=55)
 | SURVEYOR-2 |  | MAVYRET for 8 weeks (GT4 n=46; GT5 n=2; GT6 n=10)
GT1, 2, 3, 6 | VOYAGE-1 (NCT03222583) |  | MAVYRET for 8 (n=356) or 16 weeks (n=6; GT3 PRS-TE only)
TN and PRS-TE Subjects with Compensated Cirrhosis
GT1, 2, 4, 5, 6 | EXPEDITION-1 (NCT02642432) |  | MAVYRET for 12 weeks (n=146)
GT1, 2, 3, 4, 5, 6 | EXPEDITION-8 (NCT03089944) |  | MAVYRET for 8 weeks (n=343) (TN only)
GT3 | SURVEYOR-2 |  | MAVYRET for 16 weeks (PRS-TE only) (n=47)
GT5, 6 | ENDURANCE-5,6 |  | MAVYRET for 12 weeks (GT 5 n=3; GT 6 n=6)
GT1, 2, 3, 4, 6 | VOYAGE-2 (NCT03235349) |  | MAVYRET for 12 (n=157) or 16 weeks (n=3; GT3 PRS-TE only)
Subjects with CKD Stage 4 and 5 without Cirrhosis or with Compensated Cirrhosis
GT1-6 | EXPEDITION-4 (NCT02651194) |  | MAVYRET for 12 weeks (n=104)
NS5A Inhibitor or PI-Experienced Subjects without Cirrhosis or with Compensated Cirrhosis
GT1 | MAGELLAN-1 (NCT02446717) |  | MAVYRET for 12 (n=25) or 16 weeks (n=17)
HCV/HIV-1 Co-Infected Subjects without Cirrhosis or with Compensated Cirrhosis
GT1, 2, 3, 4, 6 | EXPEDITION-2 (NCT02738138) |  | MAVYRET for 8 (n=137) or 12 weeks (n=16)
Liver or Kidney Transplant Recipients without Cirrhosis
GT1, 2, 3, 4, 6 | MAGELLAN-2 (NCT02692703) |  | MAVYRET for 12 weeks (n=100)
Adolescent Subjects (12 to less than 18 years)
GT1, 2, 3, 4** | DORA (Part 1) (NCT03067129) |  | MAVYRET for 8 (n=44) or 16 weeks (n=3)
Pediatric Subjects (3 to less than 12 years)
GT1, 2, 3, 4** | DORA (Part 2) (NCT03067129) |  | MAVYRET for 8 (n=78), 12 (n=1), or 16 weeks (n=1)
Clinical Trial of Acute HCV Infection
GT1, 2, 3, 4** |  | M20-350 (NCT04903626) |  | MAVYRET for 8 weeks (n=286)
TN=treatment naïve; PI=protease inhibitor; CKD=chronic kidney disease
PRS-TE= defined as prior treatment experience with regimens containing (peg)interferon, ribavirin, and/or sofosbuvir, but no prior treatment experience with an HCV NS3/4A PI or NS5A inhibitor.
* Treatment durations for some trial arms shown in this table do not reflect recommended dosing for the respective genotypes, prior treatment history, and/or cirrhosis status. For recommended dosing in adults and pediatric patients 3 years and older [see Dosage and Administration (2.2, 2.3, 2.4)].
** ENDURANCE-1 included 33 subjects co-infected with HIV-1. DORA included 3 subjects co-infected with HIV-1. M20-350 included 142 subjects co-infected with HIV-1.

Serum HCV RNA values were measured during the clinical trials using the Roche COBAS AmpliPrep/COBAS TaqMan HCV test (version 2.0) with a lower limit of quantification (LLOQ) of 15 IU/mL (except for SURVEYOR-2 which used the Roche COBAS TaqMan real-time reverse transcriptase-PCR (RT-PCR) assay v. 2.0 with an LLOQ of 25 IU/mL). The primary endpoint across all clinical trials was sustained virologic response (SVR12), defined as HCV RNA less than LLOQ at 12 weeks after the end of treatment. Relapse was defined as HCV RNA ≥ LLOQ after end-of-treatment response among subjects who completed treatment. Subjects with missing HCV RNA data, such as those who discontinued due to an adverse event, subject withdrawal or were lost to follow-up, were counted as SVR12 failures.

Demographics and Baseline Characteristics of Clinical Trials in Adults with Chronic HCV Infection Who Were Treatment-Naïve or Treatment-Experienced to (peg)Interferon, Ribavirin and/or Sofosbuvir (PRS) without Cirrhosis or with Compensated Cirrhosis (Child-Pugh A)

Of the 2,152 subjects without cirrhosis or with compensated cirrhosis who were treatment-naïve or treatment-experienced to combinations of (peg)interferon, ribavirin and/or sofosbuvir (PRS), treated in the registrational studies excluding EXPEDITION-4 and MAGELLAN-1, the median age was 54 years (range: 19 to 88); 73% were treatment-naïve, 27% were PRS treatment-experienced; 39% had HCV genotype 1; 21% had HCV genotype 2; 29% had HCV genotype 3; 7% had HCV genotype 4; 4% had HCV genotype 5, or 6; 13% were ≥65 years; 54% were male; 5% were Black; 12% had cirrhosis; 20% had a body mass index of at least 30 kg per m^2; and median baseline HCV RNA level was 6.2 log10 IU/mL.

14.2 Treatment-Naïve or PRS Treatment-Experienced Adults with Chronic HCV Genotype 1, 2, 4, 5, or 6 Infection without Cirrhosis

The efficacy of MAVYRET in subjects who were treatment-naïve or treatment-experienced to combinations of (peg)interferon, ribavirin and/or sofosbuvir (PRS) with genotype 1, 2, 4, 5, or 6 chronic HCV infection without cirrhosis was studied in three trials using an 8-week duration: ENDURANCE-1, ENDURANCE-5,6, and SURVEYOR-2 [(Part 2 and Part 4)].

ENDURANCE-1 was a randomized (1:1), open-label, multi-national trial comparing the efficacy of 8 weeks of treatment with MAVYRET versus 12 weeks of treatment in subjects without cirrhosis with genotype 1 infection with or without HIV-1 co-infection (n=33 co-infected). Table 13 presents SVR12 in MAVYRET-treated genotype 1-infected subjects for the 8-week treatment arm. Due to numerically similar efficacy, MAVYRET is recommended for 8 weeks for treatment-naïve and PRS treatment-experienced genotype 1 subjects without cirrhosis, rather than 12 weeks [see Dosage and Administration (2.2)].

Table 13. ENDURANCE-1: Efficacy in Treatment-Naïve and PRS Treatment-Experienced Adults with Chronic HCV Genotype 1 Infection without Cirrhosis
 | MAVYRET 8 Weeks
 | GT1 N=351
SVR12 | 99% (348/351)
Outcome for Subjects without SVR12
On-treatment VF | <1% (1/351)
Relapse | 0/349
Other* | <1% (2/351)
VF= virologic failure
* Includes subjects who discontinued due to adverse event, lost to follow-up, or subject withdrawal.

The SVR12 data from the open-label trials SURVEYOR-2 (Parts 2 and 4) and ENDURANCE-5,6 are pooled by genotype, where appropriate, in Table 14 for ease of display.

Table 14. SURVEYOR-2 (Part 2 and Part 4) and ENDURANCE-5, 6: Efficacy in Treatment-Naïve and PRS Treatment-Experienced Adults with Chronic HCV Genotypes 2, 4, 5 or 6 Infection without Cirrhosis
 | MAVYRET 8 Weeks
 | GT2 N=197 | GT4 N=46 | GT5 N=22 | GT6 N=65
SVR 12 | 98% (193/197) | 93% (43/46) | 95% (21/22) | 100% (65/65)
Outcome for Subjects without SVR12
On Treatment VF | 0/197 | 0/46 | 0/22 | 0/65
Relapse | 1% (2/195) | 0/45 | 5% (1/22) | 0/65
Other* | 1% (2/197) | 7% (3/46) | 0/22 | 0/65
GT=genotype; VF= virologic failure
* Includes subjects who discontinued due to adverse event, lost to follow-up, or subject withdrawal.

14.3 Treatment-Naïve Adults with Chronic HCV Genotype 1-6 Infection with Compensated Cirrhosis or PRS Treatment-Experienced Adults with Chronic HCV Genotype 1, 2, 4, 5, or 6 Infection with Compensated Cirrhosis

The efficacy of MAVYRET in treatment-naïve subjects with genotype 1, 2, 3, 4, 5 or 6 chronic HCV infection and compensated cirrhosis (Child-Pugh A) was studied in EXPEDITION-8, a single-arm, open-label trial in 343 subjects who received MAVYRET for 8 weeks.

Table 15. EXPEDITION-8: Efficacy in Treatment-Naïve Adults with Chronic HCV Genotype 1, 2, 3, 4, 5 or 6 Infection with Compensated Cirrhosis
 | MAVYRET 8 Weeks (N=343)
 | Total (all GTs) (N=343) | GT1 (N=231) | GT2 (N=26) | GT3 (N=63) | GT4 (N=13) | GT5 (N=1) | GT6 (N=9)
SVR12 | 98% (335/343) | 98% (226/231) | 100% (26/26) | 95% (60/63) | 100% (13/13) | 100% (1/1) | 100% (9/9)
Outcome for Subjects without SVR12
On-treatment VF | 0/343 | 0/231 | 0/26 | 0/63 | 0/13 | 0/1 | 0/9
Relapse | <1% (1/336) | 0/225 | 0/26 | 2% (1/62) | 0/13 | 0/1 | 0/9
Other* | 2% (7/343) | 2% (5/231) | 0/26 | 3% (2/63) | 0/13 | 0/1 | 0/9
GT = genotype; VF = virologic failure
* Includes subjects who discontinued due to lost to follow-up or subject withdrawal.

The efficacy of MAVYRET in treatment-naive or PRS treatment-experienced subjects with genotype 1, 2, 4, 5 or 6 chronic HCV infection with compensated cirrhosis (Child-Pugh A) was studied in EXPEDITION-1 a single-arm, open-label trial, which included 146 subjects (TN N=110, TE-PRS N=36) treated with MAVYRET for 12 weeks, and in ENDURANCE-5, 6, an open-label trial in 84 subjects (TN N= 76, TE-PRS N=8) with genotype 5 or 6 chronic HCV infection, 9 of whom had compensated cirrhosis (GT5 N=3, GT6 N=6) and received MAVYRET for 12 weeks.

Table 16. EXPEDITION-1 and ENDURANCE-5, 6: Efficacy in Treatment-Naïve and PRS Treatment-Experienced Adults with Chronic HCV Genotype 1, 2, 4, 5 or 6 Infection with Compensated Cirrhosis
 | MAVYRET 12 Weeks
 | Total (all GTs) (N=155) | GT1 (N=90) | GT2 (N=31) | GT4 (N=16) | GT5 (N=5) | GT6 (N=13)
SVR12 | 99% (153/155) | 99% (89/90) | 100% (31/31) | 100% (16/16) | 100% (5/5) | 92% (12/13)
Outcome for Subjects without SVR12
On-treatment VF | <1% (1/155) | 0/90 | 0/31 | 0/16 | 0/5 | 8% (1/13)
Relapse | <1% (1/152) | 1% (1/88) | 0/31 | 0/16 | 0/5 | 0/12
GT = genotype; VF = virologic failure

14.4 Treatment-Naïve or PRS Treatment-Experienced Adults with Chronic HCV Genotype 3 Infection without Cirrhosis or with Compensated Cirrhosis

The efficacy of MAVYRET in subjects who were treatment-naïve or treatment-experienced to combinations of (peg)interferon, ribavirin and/or sofosbuvir (PRS) with genotype 3 chronic HCV infection without cirrhosis or with compensated cirrhosis was studied in ENDURANCE-3, EXPEDITION-8 and in SURVEYOR-2 Part 3. Subjects with genotype 3 HCV infection were also included in two Asian regional studies, VOYAGE-1 and VOYAGE-2.

ENDURANCE-3 was a partially-randomized, open-label, active-controlled trial in treatment-naïve subjects without cirrhosis. Subjects were randomized (2:1) to either MAVYRET for 12 weeks or to the combination of sofosbuvir and daclatasvir for 12 weeks; subsequently the trial included a third non-randomized arm with MAVYRET for 8 weeks. The SVR12 data are summarized in Table 17. Due to numerically similar efficacy, MAVYRET is recommended for 8 weeks for treatment-naïve genotype 3 subjects without cirrhosis, rather than 12 weeks [see Dosage and Administration (2.2)].

Table 17. ENDURANCE-3: Efficacy in Treatment-Naïve, Chronic HCV Genotype 3-Infected Adults without Cirrhosis
 | MAVYRET^1 8 Weeks (N=157) | MAVYRET 12 Weeks* (N=233) | DCV+SOF 12 Weeks (N=115)
SVR12 | 95% (149/157) | 95% (222/233)* | 97% (111/115)
Outcome for Subjects without SVR12
On-treatment VF | 1% (1/157) | <1% (1/233) | 0/115
Relapse | 3% (5/150) | 1% (3/222) | 1% (1/114)
Other^2 | 1% (2/157) | 3% (7/233) | 3% (3/115)
VF=virologic failure
^1 MAVYRET 8 weeks was a non-randomized treatment arm.
^2 Includes subjects who discontinued due to adverse event, lost to follow-up, or subject withdrawal.
* Data for MAVYRET 12-week treatment is displayed to reflect the original randomized study design. The treatment difference (95% confidence interval) was -1.2% (-5.6, 3.1) between the randomized arms of MAVYRET 12 weeks and DCV + SOF 12 weeks.

The efficacy of MAVYRET in subjects who were treatment-naïve with genotype 3 chronic HCV infection and compensated cirrhosis was studied in EXPEDITION-8. The SVR12 rate of the treatment-naïve subjects with genotype 3 and compensated cirrhosis was 95% (60/63) and one subject experienced virologic relapse [see Clinical Studies (14.3)].

SURVEYOR-2 Part 3 was an open-label trial randomizing PRS treatment-experienced subjects with genotype 3 infection without cirrhosis to 16-weeks of treatment. In addition, the trial evaluated the efficacy of MAVYRET in PRS treatment-experienced genotype 3-infected subjects with compensated cirrhosis for a 16-week duration. Among PRS treatment-experienced subjects treated with MAVYRET for 16 weeks, 49% (34/69) had failed a previous regimen containing sofosbuvir.

Table 18. SURVEYOR-2 Part 3: Efficacy in PRS Treatment-Experienced, Chronic HCV Genotype 3-Infected Adults without Cirrhosis or with Compensated Cirrhosis
 | PRS Treatment-Experienced without Cirrhosis or With Compensated Cirrhosis
 | MAVYRET 16 Weeks (N=69)
SVR12 | 96% (66/69)
Outcome for Subjects without SVR12
On-treatment VF | 1% (1/69)
Relapse | 3% (2/68)
Other* | 0/69
SVR12 by Cirrhosis Status
Without Cirrhosis | 95% (21/22)
With Compensated Cirrhosis | 96% (45/47)
VF=virologic failure
* Includes subjects who discontinued due to adverse event, lost to follow-up, or subject withdrawal.

Subjects with Genotype 3b Infection in VOYAGE-1 and VOYAGE-2

The efficacy of MAVYRET in subjects with HCV subtype 3b infection was evaluated in the VOYAGE-1 and VOYAGE-2 trials. Genotype 3b is a subtype that is uncommon in the U.S. (<1% of HCV GT3 infections) but has been reported in China, India and other countries in South and Southeast Asia. VOYAGE-1 and VOYAGE-2 were conducted in China, Singapore, and South Korea in HCV genotype 1, 2, 3, 4 or 6 infected subjects without cirrhosis (VOYAGE-1) or with compensated cirrhosis (VOYAGE-2) who were treatment-naive or PRS-treatment-experienced. All subjects without cirrhosis or with compensated cirrhosis received 8 or 12 weeks of MAVYRET, respectively, except genotype 3 PRS-treatment-experienced subjects who received 16 weeks of MAVYRET.

Across both trials, subjects with HCV genotype 3b infection had a numerically lower SVR12 rate of 70% (14/20) [58% (7/12) for non-cirrhotic subjects and 88% (7/8) for subjects with compensated cirrhosis] compared to subjects infected with genotype 3a or other HCV genotypes. All six genotype 3b subjects without SVR12 experienced virologic failure (2 on-treatment virologic failure, 4 relapse). SVR12 results in subjects with genotype 3a or other HCV genotypes were comparable with other trials.

14.5 Treatment-Naïve and PRS Treatment-Experienced Adults with CKD Stage 4 and 5 and Chronic HCV Infection without Cirrhosis or with Compensated Cirrhosis

EXPEDITION-4 was an open-label, single-arm, multicenter trial to evaluate safety and efficacy in subjects with severe renal impairment (CKD Stages 4 and 5) with compensated liver disease (with and without Child-Pugh A cirrhosis). There were 104 subjects enrolled, 82% were on hemodialysis, and 53%, 15%, 11%, 19%, 1% and 1% were infected with HCV genotypes 1, 2, 3, 4, 5 and 6, respectively. Overall, 19% of subjects had compensated cirrhosis and 81% of subjects were non-cirrhotic; 58% and 42% of subjects were treatment-naïve and PRS treatment-experienced, respectively. The overall SVR12 rate was 98% and no subjects experienced virologic failure. The presence of renal impairment did not affect efficacy; no dose-adjustments were required during the trial.

14.6 Adults with Chronic HCV Infection who are NS5A Inhibitor or NS3/4A-Protease Inhibitor (PI)-Experienced, without Cirrhosis or with Compensated Cirrhosis

MAGELLAN-1 was a randomized, multipart, open-label trial in 141 genotype 1- or 4-infected subjects who failed a previous regimen containing an NS5A inhibitor and/or NS3/4A PI. Part 1 (n=50) was a randomized trial exploring 12 weeks of glecaprevir 200 mg and pibrentasvir 80 mg, glecaprevir 300 mg and pibrentasvir 120 mg, with and without ribavirin (only data from glecaprevir 300 mg plus pibrentasvir 120 mg without ribavirin are included in these analyses). Part 2 (n=91) randomized genotype 1- or 4-infected subjects without cirrhosis or with compensated cirrhosis to 12- or 16-weeks of treatment with MAVYRET.

Of the 42 genotype 1-infected subjects treated in Parts 1 and 2, who were either NS5A inhibitor-experienced only (and treated for 16 weeks), or NS3/4A PI-experienced only (and treated for 12 weeks), the median age was 58 years (range: 34 to 70); 40% of the subjects were NS5A-treatment experienced only and 60% were PI experienced only; 24% had cirrhosis; 19% were ≥65 years, 69% were male; 26% were Black; 43% had a body mass index ≥ 30 kg/m^2; 67% had baseline HCV RNA levels of at least 1,000,000 IU per mL; 79% had subtype 1a infection, 17% had subtype 1b infection and 5% had non-1a/1b infection.

Due to higher rates of virologic failure and treatment-emergent drug resistance, the data do not support labeling for treatment of HCV genotype 1-infected patients who are both NS3/4A PI and NS5A inhibitor-experienced.

Table 19. MAGELLAN-1: Efficacy in HCV Genotype 1-Infected Adults with Chronic HCV Infection Who Are NS3/4A PI-Experienced or NS5A Inhibitor-Experienced, without Cirrhosis or with Compensated Cirrhosis
 | PI-Experienced^1 (NS5A Inhibitor- naïve) | NS5A Inhibitor- Experienced^2 (PI-naïve)
 | MAVYRET 12 Weeks (N=25) | MAVYRET 16 Weeks (N=17)
SVR12 | 92% (23/25) | 94% (16/17)
Outcome for Subjects without SVR
On-treatment Virologic Failure | 0/25 | 6% (1/17)
Relapse | 0/25 | 0/16
Other^3 | 8% (2/25) | 0/17
PI= protease inhibitor
^1 Includes subjects who were treated with a regimen containing an NS3/4A PI (simeprevir with sofosbuvir, or simeprevir, boceprevir, or telaprevir with (peg)interferon and ribavirin) and without prior treatment with an NS5A inhibitor.
^2 Includes subjects who were treated with a regimen containing an NS5A inhibitor (ledipasvir with sofosbuvir or daclatasvir with (peg)interferon and ribavirin) and without prior treatment with an NS3/4A PI.
^3 Includes subjects who discontinued due to adverse event, lost to follow-up, or subject withdrawal.

14.7 Treatment-Naïve or PRS Treatment-Experienced Adults with Chronic HCV/HIV-1 Coinfection without Cirrhosis or with Compensated Cirrhosis

EXPEDITION-2 was an open-label study in 153 HCV/HIV-1-coinfected subjects. Subjects without cirrhosis received MAVYRET for 8 weeks and subjects with compensated cirrhosis received MAVYRET for 12 weeks. The study included subjects who were HCV treatment-naïve or treatment-experienced to combinations of (peg)interferon, ribavirin, and/or sofosbuvir, with the exception of genotype 3-infected subjects who were all treatment naïve.

Of the 153 subjects treated, the median age was 45 years (range: 23 to 74); 63% had HCV genotype 1, 7% had HCV genotype 2, 17% had HCV genotype 3, 11% had HCV genotype 4, 2% had HCV genotype 6; 11% had cirrhosis; 84% were male; and 16% were Black.

In EXPEDITION-2, the SVR12 rate in HCV/HIV-1 co-infected subjects was 98% (150/153). One subject experienced on-treatment virologic failure and no subjects relapsed.

14.8 Treatment-Naïve or PRS Treatment-Experienced Adults with Chronic HCV Infection with Liver or Kidney Transplant without Cirrhosis

MAGELLAN-2 was a single-arm, open-label study in 100 post-liver or -kidney transplant HCV genotype 1, 2, 3, 4, or 6 infected subjects without cirrhosis who received MAVYRET for 12 weeks. The study included subjects who were HCV treatment-naïve or treatment-experienced to combinations of (peg)interferon, ribavirin, and/or sofosbuvir, with the exception of genotype 3-infected subjects who were all treatment-naïve.

Of the 100 subjects treated, the median age was 60 years (range: 39 to 78); 57% had HCV genotype 1, 13% had HCV genotype 2, 24% had HCV genotype 3, 4% had HCV genotype 4, 2% had HCV genotype 6; 75% were male; 8% were Black; 80% of subjects were post-liver transplant and 20% were post-kidney transplant. Immunosuppressants allowed for co-administration were cyclosporine ≤100 mg, tacrolimus, sirolimus, everolimus, azathioprine, mycophenolic acid, prednisone, and prednisolone.

The overall SVR12 rate in post-transplant subjects was 98% (98/100). There was one relapse and no on-treatment virologic failures.

14.9 People Who Inject Drugs (PWID) and those on Medication-Assisted Treatment (MAT) for Opioid Use Disorder with Chronic HCV Infection

PWID

Among 4,655 chronic HCV genotype 1-6-infected adolescents and adults in Phase 2 and 3 trials who received MAVYRET and specified whether or not they had a history of injection drug use, 1,373 subjects were identified as PWID based on self-reported history of injection drug use at trial enrollment and 3,282 subjects did not report injection drug use (non-PWID). Of the PWID population, 62 subjects were considered current/recent PWID (defined as self-reported injection drug use within the last 12 months prior to starting MAVYRET), 959 subjects were considered former PWID (defined as self-reported injection drug use more than 12 months prior to starting MAVYRET), and 352 subjects did not specify current/recent PWID versus former PWID and were not included in the analysis. Compared to former/non-PWID subjects (n=4,241), the current/recent PWID subjects were more frequently male (79%), White (73%), younger (median age [range]: 40 years [19 to 64]), treatment-naïve (94%), and had higher proportions of HCV genotype 3 infection (44%) and HIV co-infection (24%). Similar to the former/non-PWID subjects, the majority of current/recent PWID subjects were non-cirrhotic (73%). The overall SVR12 rate was 98% in former/non-PWID subjects and 89% in current/recent PWID subjects; the difference between the two groups was primarily due to missing data at the time of the SVR12 measurement window in the current/recent PWID group. Virologic failure rates, however, were similar in both groups: 2% in the current/recent PWID subjects and 1% in former/non-PWID subjects.

MAT

Among 4,655 chronic HCV genotype 1-6-infected adolescents and adults in Phase 2 and 3 trials who received MAVYRET and specified whether or not they had a history of injection drug use, 225 subjects reported concomitant use of MAT for opioid use disorder and 4,098 subjects reported no use of MAT (332 subjects were not included in the analysis due to missing assessment of MAT). Compared to those not on MAT, subjects on MAT were more frequently male (70%), White (92%), younger (median age [range]: 47 years [23 to 76]), treatment-naïve (89%), and had a higher proportion of HCV genotype 3 infection (50%). Of subjects on MAT, 74% were non-cirrhotic, and 7% were co-infected with HIV, similar to those not on MAT. The SVR12 rates were similar between subjects on MAT (96%) and those not on MAT (98%), with low rates of virologic failure in both groups (<1% and 1%, respectively).

14.10 Clinical Trial in Pediatric Subjects 3 Years and Older with Chronic HCV Infection

The efficacy of MAVYRET was evaluated in an open-label study (DORA [Part 1 and Part 2]) that evaluated pediatric subjects 3 years to less than 18 years without cirrhosis who received MAVYRET for 8, 12, or 16 weeks. Treatment duration was chosen to match approved adult durations based on HCV genotype and prior treatment experience.

DORA Part 1

Forty-seven subjects were enrolled in DORA (Part 1) and received the adult dose of MAVYRET tablets. The median age was 14 years (range: 12 years to 17 years); the mean weight was 59 kg (range: 32 kg to 109 kg); 55% were female; 74% were White; 13% were Asian, and 9% were Black; 79% had HCV genotype 1, 6% had HCV genotype 2, 9% had HCV genotype 3, and 6% had HCV genotype 4; 77% were HCV TN; 23% were treatment-experienced to interferon; 4% had HIV-coinfection; none had cirrhosis. The overall SVR12 rate was 100% (47/47).

DORA Part 2

Eighty subjects aged 3 years to less than 12 years were enrolled in DORA (Part 2) and received weight-based dosing of MAVYRET oral pellets for 8, 12, or 16 weeks. The median age was 7 years (range: 3 years to 11 years); the mean weight was 26 kg (range: 13 kg to 44 kg); 55% were female; 69% were White, 18% were Asian, and 4% were Black; 73% had HCV genotype 1, 3% had HCV genotype 2, 23% had HCV genotype 3, and 3% had HCV genotype 4; 97.5% were HCV TN; 2.5% were treatment-experienced to interferon; 1% had HIV-coinfection; none had cirrhosis.

Sixty-two subjects received the weight-based recommended dosage. Eighteen subjects received doses lower than the recommended weight-based dosage and were not included in the efficacy assessment. The overall SVR12 rate for the subjects who received the recommended dosage was 98.4% (61/62); the subject who did not achieve SVR12 discontinued treatment due to an adverse reaction [see Adverse Reactions (6.1)].

14.11 Adults with Acute HCV Infection

The efficacy of MAVYRET in subjects with documented acute HCV infection was evaluated in M20-350, a single-arm, open-label study of 286 adults who were treatment-naïve for the current infection and received MAVYRET for 8 weeks.

Diagnosis of acute HCV infection at screening was based on physician diagnosis, quantifiable HCV RNA, and one or more of the following: negative anti-HCV antibody, recent conversion of negative to positive results in anti-HCV antibody, HCV RNA or HCV core antigen testing, liver disease signs associated with acute HCV infection, and recent risk behaviors for HCV infection. Eighty-four percent of enrolled subjects had evidence of clinical hepatitis at screening in the absence of other causes of liver disease and with recent risk behavior for HCV transmission. At baseline, 96% of subjects had quantifiable HCV RNA, of whom 39% had a documented result of negative HCV antibody or unquantifiable HCV RNA within the previous year, and 4% of subjects had unquantifiable HCV RNA possibly reflecting spontaneous clearance of the HCV infection during the pre-treatment period.

The median age was 43 years (range: 20 to 78); 18% had a history of a prior HCV infection; 58% had HCV genotype 1, 4% had HCV genotype 2, 12% had HCV genotype 3, 17% had HCV genotype 4; 6% were ≥65 years; 89% were male; 11% were Black; 2% had cirrhosis; 50% had HIV co-infection; 14% were current/recent PWID; 7% reported ongoing use of MAT for opioid use disorder, 9% had a body mass index of at least 30 kg per m^2; and median baseline HCV RNA level was 5.4 log10 IU/mL.

The overall SVR12 rate was 96% (275/286); no subjects experienced virologic failure. Two subjects who did not achieve SVR12 likely were reinfected with HCV based on having different HCV genotypes or subtype clades between the baseline and follow-up periods.

16 HOW SUPPLIED/STORAGE AND HANDLING

MAVYRET Tablets

Configuration | Content | Package Size | NDC
Monthly carton (blister pack) | 4 weekly cartons 7 daily blisters/carton 3 tablets/blister | 84 tablets | 0074-2625-04
Monthly carton (wallet) | 4 weekly cartons 7 daily wallets/carton 3 tablets/wallet | 84 tablets | 0074-2625-28
8-Week Carton | 2 monthly cartons 4 weekly cartons/monthly carton 7 daily wallets/carton 3 tablets/wallet | 168 tablets | 0074-2625-56
Bottle |  | 84 tablets | 0074-2625-84

MAVYRET tablets are pink-colored, film-coated, oblong biconvex shaped, debossed with “NXT” on one side.

Store at or below 30°C (86°F).

MAVYRET Oral Pellets

MAVYRET oral pellets are dispensed in child-resistant unit-dose packets in cartons. Each carton contains 28 packets. Each packet contains 50 mg glecaprevir/20 mg pibrentasvir pink and yellow oral pellets. The NDC number is 0074-2600-28.

Store at or below 30°C (86°F).

17 PATIENT COUNSELING INFORMATION

Advise the patient to read the FDA-approved patient labeling (Patient Information).

Risk of Hepatitis B Virus Reactivation in Patients Coinfected with HCV and HBV

Inform patients that HBV reactivation can occur in patients coinfected with HBV during or after treatment of HCV infection. Advise patients to tell their healthcare provider if they have a history of hepatitis B virus infection [see Warnings and Precautions (5.1)].

Risk of Hepatic Decompensation/Failure in Patients with Evidence of Advanced Liver Disease

Advise patients to seek medical evaluation immediately for symptoms of worsening liver problems such as nausea, tiredness, yellowing of the skin or white part of the eyes, bleeding or bruising more easily than normal, confusion, loss of appetite, diarrhea, dark or brown urine, dark or bloody stool, swelling of the stomach area (abdomen) or pain in the upper right side of the stomach area, sleepiness, or vomiting of blood [see Warnings and Precautions (5.2)].

Drug Interactions

Inform patients that MAVYRET may interact with some drugs; therefore, patients should be advised to report to their healthcare provider the use of any prescription, non-prescription medication or herbal products [see Contraindications (4), Warnings and Precautions (5.3) and Drug Interactions (7)].

Administration

For MAVYRET oral pellets, advise patients or caregivers to read and follow the Instructions for Use for preparing the correct dose [see Dosage and Administration (2.4, 2.5)].

Inform patients it is important to take all three tablets at the same time once daily with food as directed. Inform patients that it is important not to miss or skip doses and to take MAVYRET for the duration that is recommended by the physician [see Dosage and Administration (2.2)].

If a dose is missed and it is:

- Less than 18 hours from the usual time that MAVYRET should have been taken – advise the patient to take the dose as soon as possible and then to take the next dose at the usual time.
- More than 18 hours from the usual time that MAVYRET should have been taken – advise the patient not to take the missed dose and to take the next dose at the usual time.

Manufactured by AbbVie Inc., North Chicago, IL 60064

MAVYRET and its design are trademarks of AbbVie Inc.

© 2025 AbbVie Inc. All rights reserved.

20092779

Patient Information

MAVYRET® (MAV-ih-reht)
(glecaprevir and pibrentasvir)
tablets

MAVYRET® (MAV-ih-reht)
(glecaprevir and pibrentasvir)
oral pellets

What is the most important information I should know about MAVYRET?
MAVYRET can cause serious side effects, including:
Hepatitis B virus reactivation. Before starting treatment with MAVYRET, your healthcare provider will do blood tests to check for hepatitis B virus infection. If you have ever had hepatitis B virus infection, the hepatitis B virus could become active again during or after treatment for hepatitis C virus with MAVYRET. Hepatitis B virus that becomes active again (called reactivation) may cause serious liver problems including liver failure and death. Your healthcare provider will monitor you if you are at risk for hepatitis B virus reactivation during treatment and after you stop taking MAVYRET.
For more information about side effects, see the section “What are the possible side effects of MAVYRET?”

What is MAVYRET?
MAVYRET is a prescription medicine used to treat adults and children 3 years of age and older with:

- acute (recently infected) or chronic (lasting a long time) hepatitis C virus (HCV) genotypes 1, 2, 3, 4, 5 or 6 infection without cirrhosis or with compensated cirrhosis.
- HCV genotype 1 infection who have been previously treated with a regimen that contained an HCV NS5A inhibitor or an NS3/4A protease inhibitor (PI), but not both.

MAVYRET contains the 2 medicines: glecaprevir and pibrentasvir.
It is not known if MAVYRET is safe and effective in children under 3 years of age.

Do not take MAVYRET if you:

- have certain liver problems
- also take any of the following medicines:
  ○ atazanavir
  ○ rifampin

Before taking MAVYRET, tell your healthcare provider about all of your medical conditions, including if you:

- have had hepatitis B virus infection
- have liver problems other than hepatitis C virus infection
- have HIV-1 infection
- have had a liver or a kidney transplant
- are pregnant or plan to become pregnant. It is not known if MAVYRET will harm your unborn baby.
- are breastfeeding or plan to breastfeed. It is not known if MAVYRET passes into your breast milk. Talk to your healthcare provider about the best way to feed your baby during treatment with MAVYRET.

Tell your healthcare provider about all the medicines you take, including prescription and over-the-counter medicines, vitamins, and herbal supplements.
MAVYRET and other medicines may affect each other. This can cause you to have too much or not enough MAVYRET or other medicines in your body. This may affect the way MAVYRET or your other medicines work or may cause side effects.
Keep a list of your medicines to show your healthcare provider and pharmacist.

- You can ask your healthcare provider or pharmacist for a list of medicines that interact with MAVYRET.
- Do not start taking a new medicine without telling your healthcare provider. Your healthcare provider can tell you if it is safe to take MAVYRET with other medicines.

How should I take MAVYRET?

- Take MAVYRET exactly as your healthcare provider tells you to take it. Do not change your dose unless your healthcare provider tells you to.
- Do not stop taking MAVYRET without first talking with your healthcare provider.
- Do not miss or skip doses of MAVYRET during treatment.
- Take MAVYRET with food.
- For adults, adolescents 12 years and older, or children weighing at least 99 pounds (45 kg), the usual dose of MAVYRET is 3 tablets at the same time each day.
- For children 3 years to less than 12 years of age and weighing less than 99 pounds (45 kg), your child’s healthcare provider will prescribe the right dose of MAVYRET oral pellets based on your child’s body weight.
  - If your child’s healthcare provider prescribes MAVYRET oral pellets for your child, see “How should I give MAVYRET oral pellets to my child?”
- If you miss a dose of MAVYRET and it is:
  - Less than 18 hours from the time you usually take MAVYRET, take the missed dose with food as soon as possible. Then take your next dose at your usual time.
  - More than 18 hours from the time you usually take MAVYRET, do not take the missed dose. Take your next dose at your usual time with food.
- If you take too much MAVYRET, call your healthcare provider or go to the nearest hospital emergency room right away.

How should I give MAVYRET oral pellets to my child?
See the detailed Instructions for Use for information about how to give or take a dose of MAVYRET oral pellets.

- Give MAVYRET oral pellets exactly as instructed by your healthcare provider.
- Give MAVYRET 1 time a day just before or after a snack or meal.
- Do not open the packet until ready to use.
- Mix the pellets with a small amount of recommended food and swallow (see Instructions for Use for list of recommended food).
- Swallow the food and oral pellets mixture within 15 minutes of preparation. Do not crush or chew the oral pellets.
- Do not store any leftover mixture (MAVYRET oral pellets mixed with food) for use at a later time. Throw away any unused portion.

What are the possible side effects of MAVYRET?
MAVYRET can cause serious side effects, including:

- Hepatitis B virus reactivation. See “What is the most important information I should know about MAVYRET?”
- In people who had or have advanced liver problems before starting treatment with MAVYRET: rare risk of worsening liver problems, liver failure and death. Your healthcare provider will check you for signs and symptoms of worsening liver problems during treatment with MAVYRET. Tell your healthcare provider right away if you have any of the following signs and symptoms:

- nausea
- tiredness
- yellowing of your skin or white part of your eyes
- bleeding or bruising more easily than normal
- confusion
- dark, black, or bloody stool
- loss of appetite

- diarrhea
- dark or brown (tea-colored) urine
- swelling or pain on the upper right side of your stomach area (abdomen)
- sleepiness
- vomiting of blood
- lightheadedness

The most common side effects of MAVYRET include headache and tiredness.
These are not all the possible side effects of MAVYRET.
Call your doctor for medical advice about side effects. You may report side effects to FDA at 1-800-FDA-1088.

How should I store MAVYRET?

- Store MAVYRET at or below 86°F (30°C).
- Keep MAVYRET in its original package until you are ready to take it.

Keep MAVYRET and all medicines out of the reach of children.

General information about the safe and effective use of MAVYRET
Medicines are sometimes prescribed for purposes other than those listed in a Patient Information leaflet. Do not use MAVYRET for a condition for which it was not prescribed. Do not give MAVYRET to other people, even if they have the same symptoms that you have. It may harm them. You can ask your healthcare provider or pharmacist for information about MAVYRET that is written for health professionals.

What are the ingredients in MAVYRET?
MAVYRET tablets
Active ingredients: glecaprevir and pibrentasvir
Inactive ingredients: colloidal silicon dioxide, copovidone (type K 28), croscarmellose sodium, hypromellose 2910, iron oxide red, lactose monohydrate, polyethylene glycol 3350, propylene glycol monocaprylate (type II), sodium stearyl fumarate, titanium dioxide, and vitamin E (tocopherol) polyethylene glycol succinate. The tablets do not contain gluten.
MAVYRET oral pellets:
Active ingredients: glecaprevir and pibrentasvir
Inactive ingredients: colloidal silicon dioxide, copovidone (type K 28), croscarmellose sodium, hypromellose 2910, iron oxide red, iron oxide yellow, lactose monohydrate, polyethylene glycol/macrogol 3350, propylene glycol monocaprylate (type II), sodium stearyl fumarate, titanium dioxide, vitamin E (tocopherol) polyethylene glycol succinate. The oral pellets do not contain gluten.
Manufactured by AbbVie Inc., North Chicago, IL 60064.
MAVYRET and its design are trademarks of AbbVie Inc.
For more information go to www.MAVYRET.com or call 1-800-633-9110.

This Patient Information has been approved by the U.S. Food and Drug Administration.
20092779

Revised: June 2025

INSTRUCTIONS FOR USE

MAVYRET® (MAV-ih-reht)
(glecaprevir and pibrentasvir)
pellets for oral use

PRINCIPAL DISPLAY PANEL

NDC 0074-2625-04

Rx only

MAVYRET®

(glecaprevir and pibrentasvir)

100mg / 40mg

Each tablet contains glecaprevir and pibrentasvir 100mg / 40mg.

This carton contains 21 tablets packaged as follows: 7 daily blisters for 1 week of treatment.

Each daily blister contains 3 tablets.

MON TUE WED THU FRI SAT SUN

Track your daily treatment by pushing in the tab above after removing each pack from carton.

PRINCIPAL DISPLAY PANEL

NDC 0074-2625-04 4-WEEK SUPPLY

Rx only

MAVYRET®

(glecaprevir and pibrentasvir)

100mg / 40mg

Each tablet contains glecaprevir and pibrentasvir 100mg / 40mg.

This monthly carton contains 84 tablets packaged as follows: 4 weekly cartons of therapy.

Each weekly carton contains 21 tablets in 7 daily blisters of 3 tablets each.

PRINCIPAL DISPLAY PANEL

NDC 0074-2625-28

Rx only

Mavyret®

(glecaprevir and pibrentasvir)
100mg / 40mg

Each tablet contains glecaprevir and pibrentasvir 100mg / 40mg.

This carton contains 21 tablets packaged as follows: 7 wallets for 1 week of treatment.

Each wallet contains 3 tablets.

MON TUE WED THU FRI SAT SUN
Track your daily treatment by pushing in the tab above after removing each pack from carton.

PRINCIPAL DISPLAY PANEL

NDC 0074-2625-28

Rx only

4-WEEK SUPPLY

Mavyret®
(glecaprevir and pibrentasvir)
100mg / 40mg

Each tablet contains glecaprevir and pibrentasvir 100mg / 40mg

This monthly carton contains 84 tablets packaged as follows: 4 weekly cartons of therapy.
Each weekly carton contains 21 tablets in 7 wallets of 3 tablets each.

PRINCIPAL DISPLAY PANEL

NDC 0074-2600-28

Rx only

MAVYRET®

(glecaprevir/pibrentasivir) Oral Pellets

50 mg/20 mg

Each packet contains pink and yellow oral pellets.

28 packets